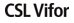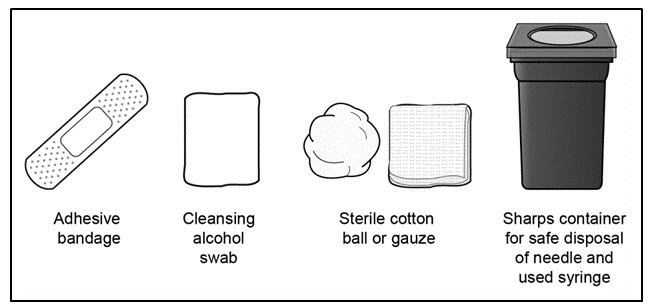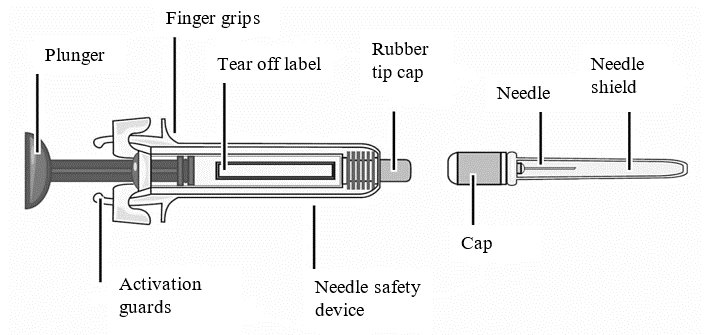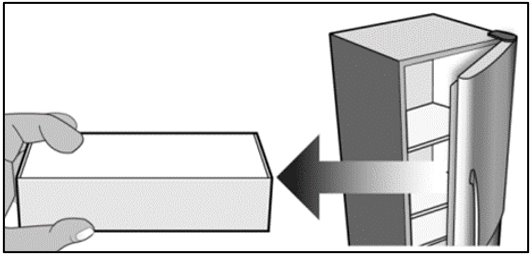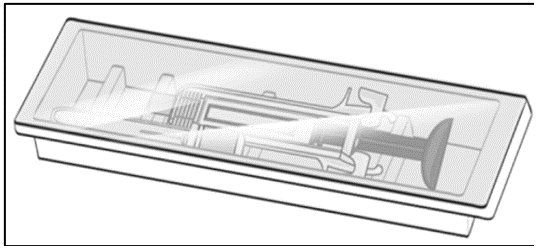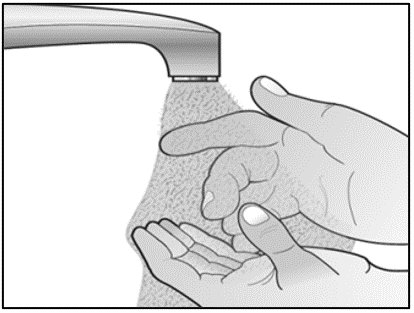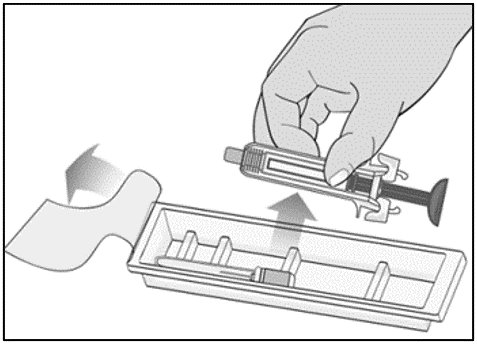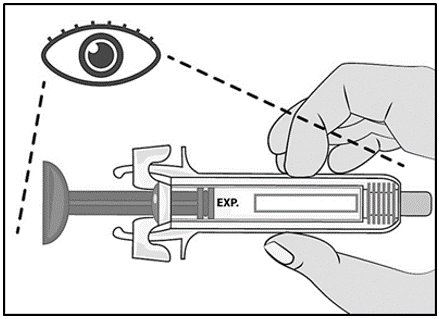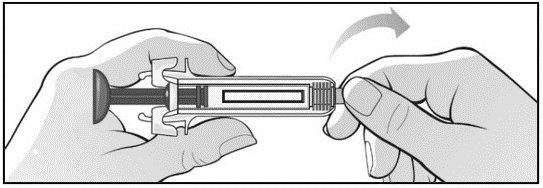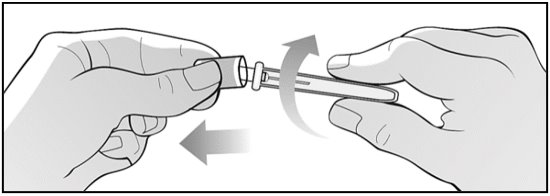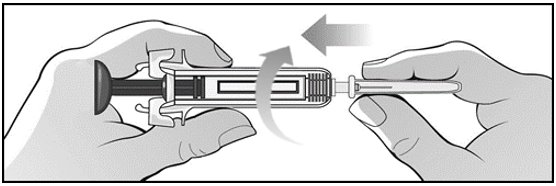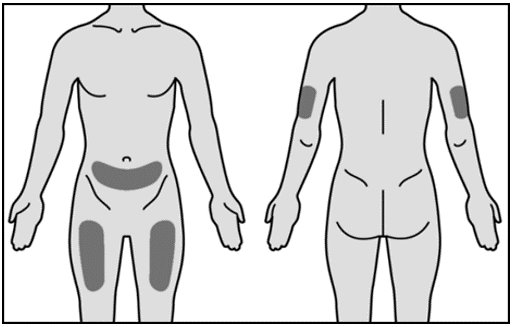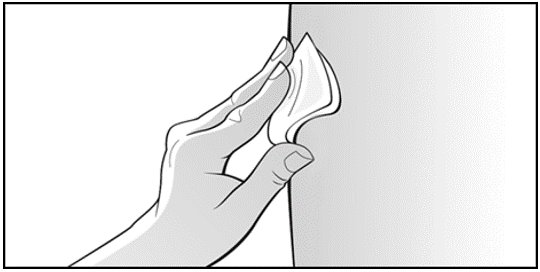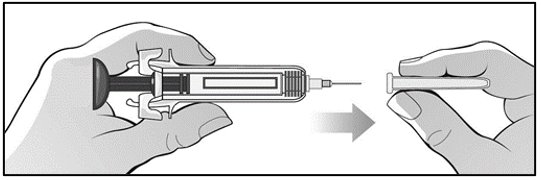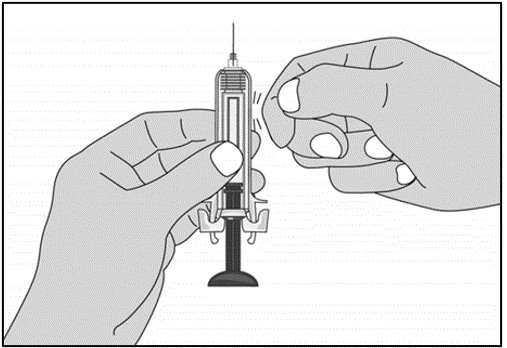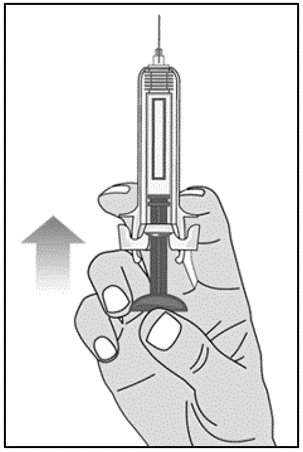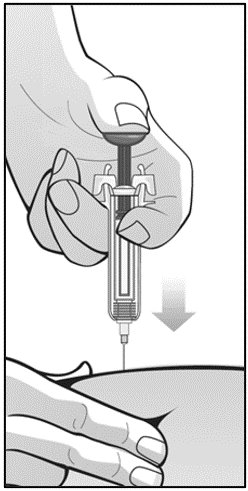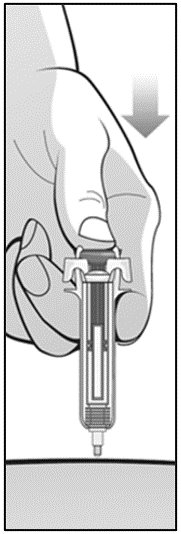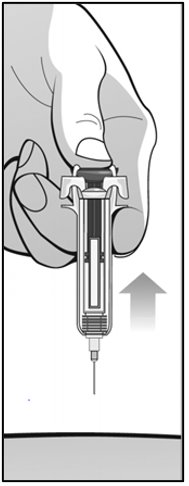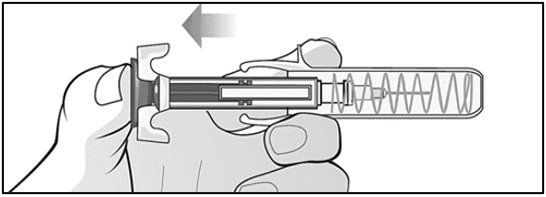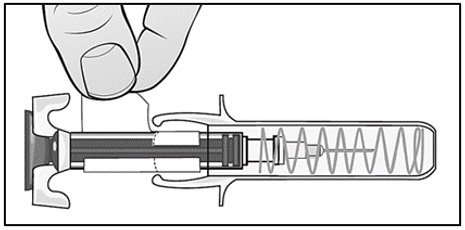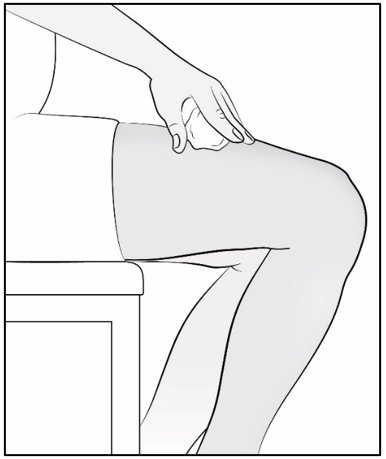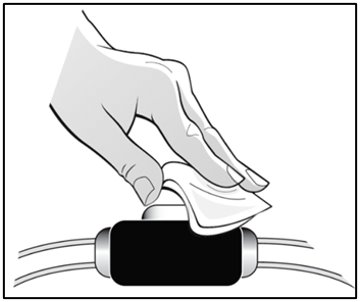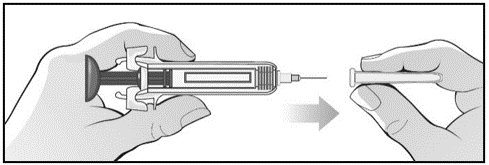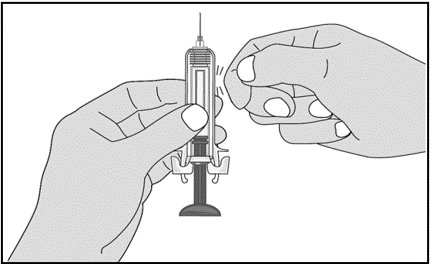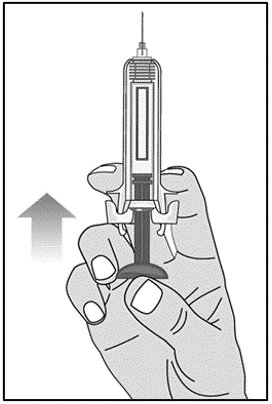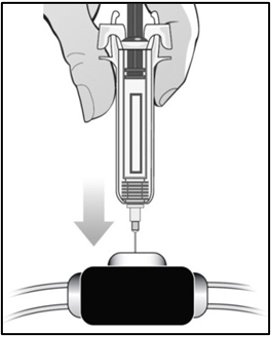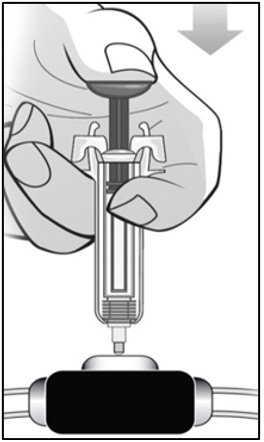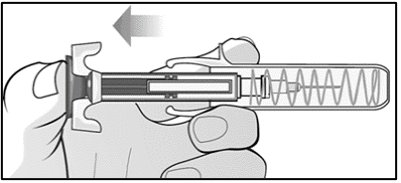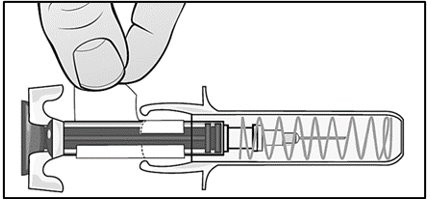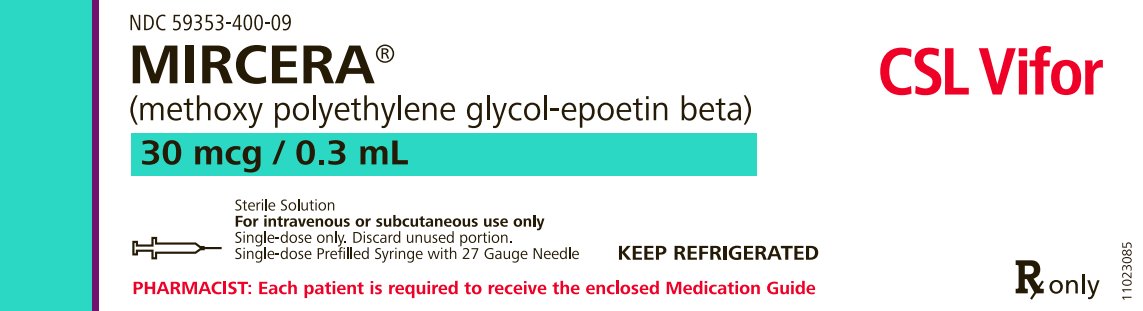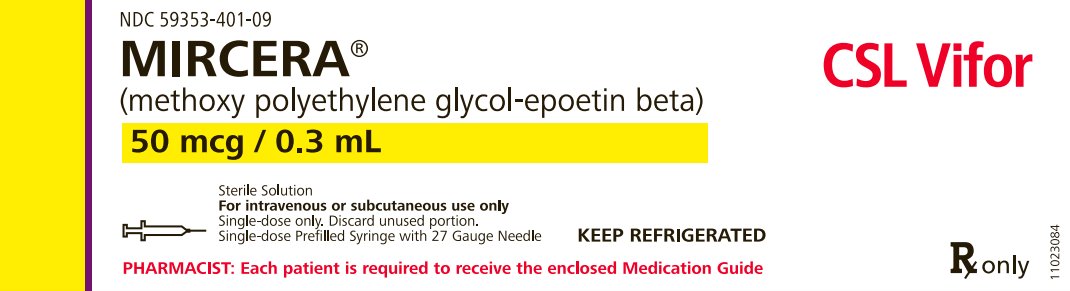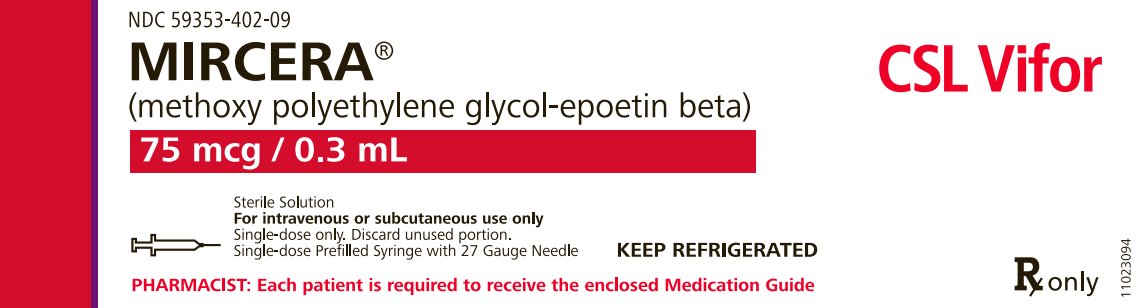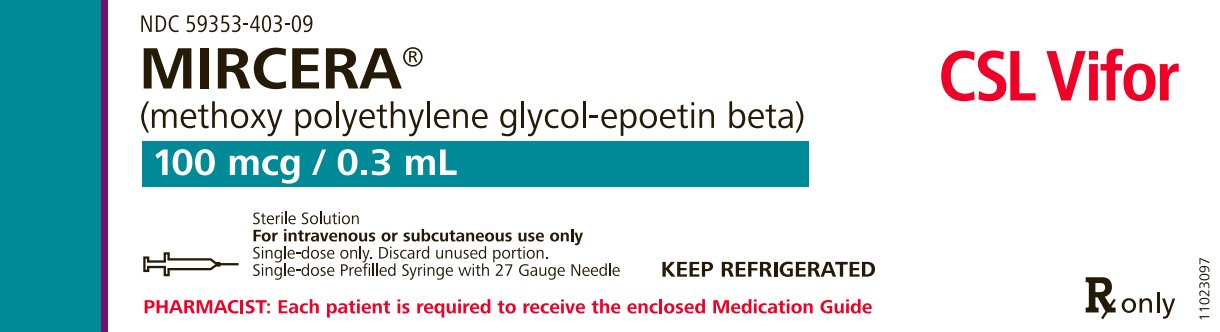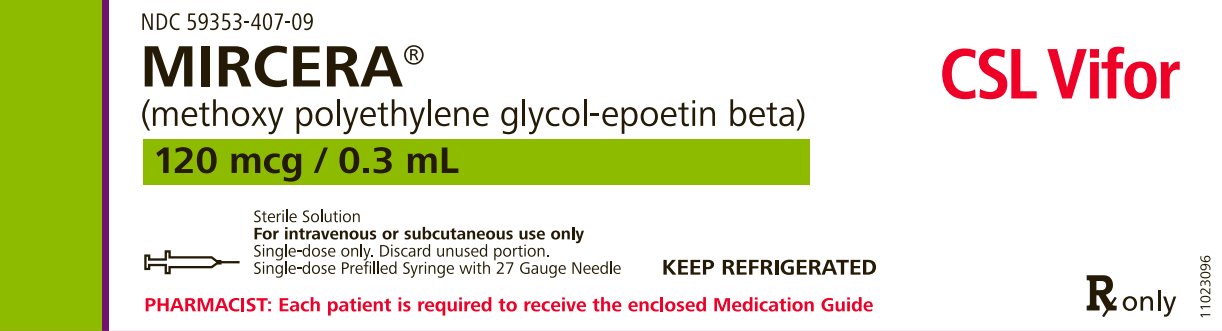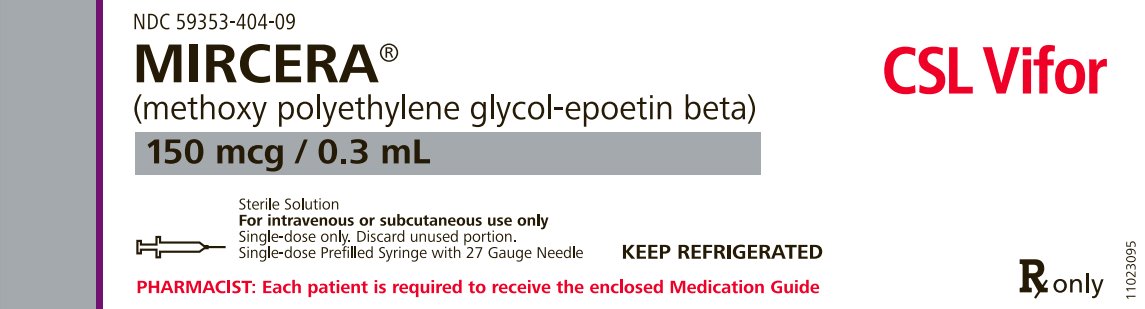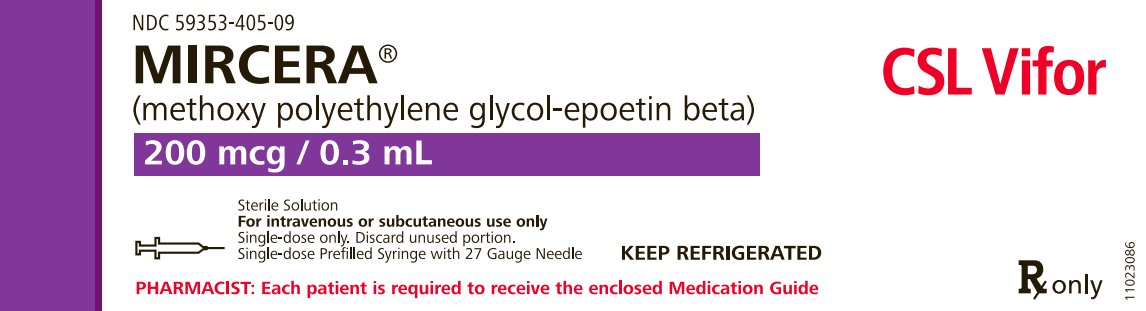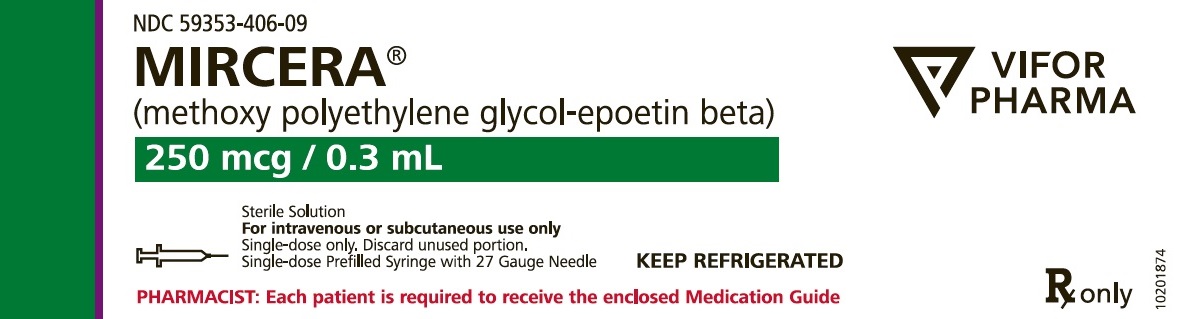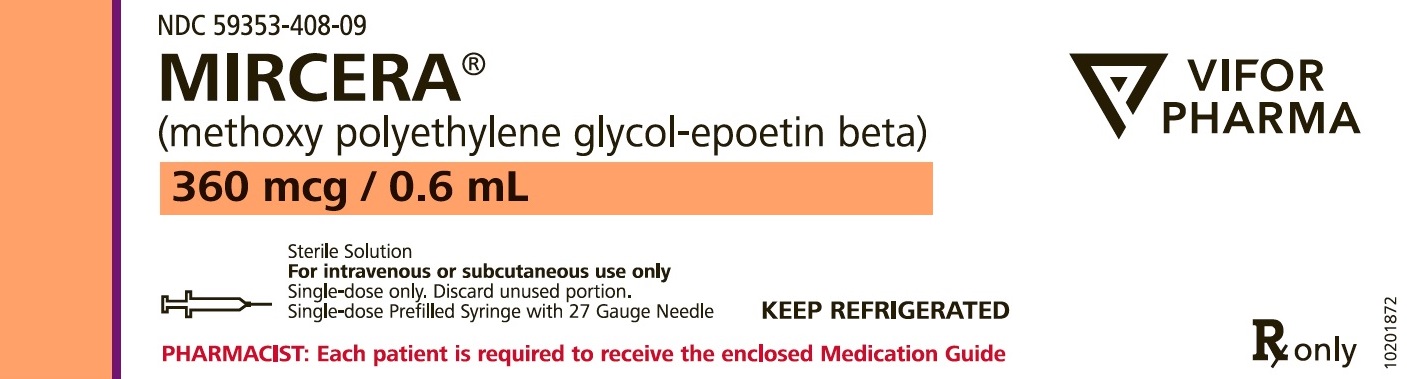 DRUG LABEL: Mircera
NDC: 59353-400 | Form: INJECTION, SOLUTION
Manufacturer: Vifor (International) Inc.
Category: prescription | Type: HUMAN PRESCRIPTION DRUG LABEL
Date: 20240605

ACTIVE INGREDIENTS: Methoxy polyethylene glycol-epoetin beta 30 ug/0.3 mL
INACTIVE INGREDIENTS: SODIUM PHOSPHATE, MONOBASIC, UNSPECIFIED FORM; sodium sulfate anhydrous; mannitol; methionine; poloxamer 188

HIGHLIGHTS OF PRESCRIBING INFORMATION

These highlights do not include all the information needed to use MIRCERA safely and effectively. See full prescribing information for MIRCERA.
MIRCERA® (methoxy polyethylene glycol-epoetin beta) injection, for intravenous or subcutaneous use
Initial U.S. Approval: 2007

RECENT MAJOR CHANGES

Indication and Usage (1) | 04/2024
Dosage and Administration (2.2) | 04/2024

WARNING: ESAs INCREASE THE RISK OF DEATH, MYOCARDIAL INFARCTION, STROKE, VENOUS THROMBOEMBOLISM, THROMBOSIS OF VASCULAR ACCESS and TUMOR PROGRESSION OR RECURRENCE

See full prescribing information for complete boxed warning

Chronic Kidney Disease:

- In controlled trials, patients experienced greater risks for death, serious adverse cardiovascular reactions, and stroke when administered erythropoiesis-stimulating agents (ESAs) to target a hemoglobin level of greater than 11 g/dL (5.1).
- No trial has identified a hemoglobin target level, ESA dose, or dosing strategy that does not increase these risks (5.1).
- Use the lowest Mircera dose sufficient to reduce the need for red blood cell (RBC) transfusions (5.1).

Cancer:

- Mircera is not indicated and is not recommended for the treatment of anemia due to cancer chemotherapy. A dose-ranging study of Mircera was terminated early because of more deaths among patients receiving Mircera than another ESA (5.2).
- ESAs shortened overall survival and/or increased the risk of tumor progression or recurrence in clinical studies in patients with breast, non-small cell lung, head and neck, lymphoid, and cervical cancers (5.2).

1 INDICATIONS AND USAGE

Mircera is an erythropoiesis-stimulating agent (ESA) indicated for the treatment of anemia associated with chronic kidney disease (CKD) in:

- adult patients on dialysis and adult patients not on dialysis (1.1).
- pediatric patients 3 months to 17 years of age on dialysis or not on dialysis who are converting from another ESA after their hemoglobin level was stabilized with an ESA (1.1).

Limitations of Use

Mircera is not indicated and is not recommended for use:

- In the treatment of anemia due to cancer chemotherapy (5.2).
- As a substitute for RBC transfusions in patients who require immediate correction of anemia (12.2).

Mircera has not been shown to improve quality of life, fatigue, or patient well-being.

2 DOSAGE AND ADMINISTRATION

Mircera is administered by subcutaneous or intravenous injection (2.2).

Adult Patients

- Initial Treatment: (patients not currently treated with an ESA):
  - CKD patients on dialysis: 0.6 mcg/kg body weight administered once every two weeks (2.2).
  - CKD patients not on dialysis: 1.2 mcg/kg body weight administered once every month as a single subcutaneous injection. Alternatively, a starting dose of 0.6 mcg/kg body weight may be administered once every two weeks as a single intravenous or subcutaneous injection (2.2).
- Conversion from Another ESA:
  - Dosed once monthly or once every two weeks based on total weekly epoetin alfa or darbepoetin alfa dose at time of conversion (2.2).

Pediatric Patients

- Conversion from another ESA: dosed once every 4 weeks based on total weekly epoetin alfa or darbepoetin alfa dose at time of conversion (2.2).
- In patients less than 6 years of age, maintain the same route of administration as the previous ESA when switching from another ESA to Mircera.

3 DOSAGE FORMS AND STRENGTHS

- Injection: 30 mcg, 50 mcg, 75 mcg, 100 mcg, 120 mcg, 150 mcg, 200 mcg, or 250 mcg in 0.3 mL solution in single-dose prefilled syringes (3).
- Injection: 360 mcg in 0.6 mL solution in single-dose prefilled syringes (3).

4 CONTRAINDICATIONS

- Uncontrolled hypertension (4).
- Pure red cell aplasia (PRCA) that begins after treatment with Mircera or other erythropoietin protein drugs (4).
- History of serious allergic reactions to Mircera, including anaphylaxis (4).

5 WARNINGS AND PRECAUTIONS

- Hypertension: Control hypertension prior to initiating and during treatment with Mircera (5.3).
- Seizures: Seizures have occurred in CKD patients participating in Mircera clinical studies. Increase monitoring of these patients for changes in seizure frequency or premonitory symptoms (5.4).
- PRCA: If severe anemia and low reticulocyte count develop during Mircera treatment, withhold Mircera and evaluate for PRCA (5.6).
- Serious Allergic Reactions: Discontinue Mircera and manage reactions (5.7).
- Severe Cutaneous Reactions: Discontinue Mircera (5.8).

6 ADVERSE REACTIONS

The most common adverse reactions (≥ 10%) are hypertension, diarrhea, nasopharyngitis (6).

To report SUSPECTED ADVERSE REACTIONS, contact Vifor (International) Inc. at 1-800-576-8295, or FDA at 1-800-FDA-1088 or www.fda.gov/medwatch.

FULL PRESCRIBING INFORMATION

WARNING: ESAs INCREASE THE RISK OF DEATH, MYOCARDIAL INFARCTION, STROKE, VENOUS THROMBOEMBOLISM, THROMBOSIS OF VASCULAR ACCESS and TUMOR PROGRESSION OR RECURRENCE

Chronic Kidney Disease [see Warnings and Precautions (5.1)]

- In controlled trials, patients experienced greater risks for death, serious adverse cardiovascular reactions, and stroke when administered erythropoiesis-stimulating agents (ESAs) to target a hemoglobin level of greater than 11 g/dL.
- No trial has identified a hemoglobin target level, ESA dose, or dosing strategy that does not increase these risks.
- Use the lowest Mircera dose sufficient to reduce the need for red blood cell (RBC) transfusions.

Cancer [see Warnings and Precautions (5.2)]

- Mircera is not indicated and is not recommended for the treatment of anemia due to cancer chemotherapy. A dose-ranging study of Mircera was terminated early because of more deaths among patients receiving Mircera than another ESA.
- ESAs have shown shortened overall survival and/or increased the risk of tumor progression or recurrence in clinical studies in patients with breast, non-small cell lung, head and neck, lymphoid, and cervical cancers.

1 INDICATIONS AND USAGE

1.1 Anemia Due to Chronic Kidney Disease

Mircera is indicated for the treatment of anemia associated with chronic kidney disease (CKD) in:

- adult patients on dialysis and adult patients not on dialysis.
- pediatric patients 3 months to 17 years of age on dialysis or not on dialysis who are converting from another ESA after their hemoglobin level was stabilized with an ESA.

Limitations of Use

Mircera is not indicated and is not recommended:

- In the treatment of anemia due to cancer chemotherapy [see Warnings and Precautions (5.2)].
- As a substitute for RBC transfusions in patients who require immediate correction of anemia [see Clinical Pharmacology (12.2)].

Mircera has not been shown to improve symptoms, physical functioning, or health-related quality of life.

2 DOSAGE AND ADMINISTRATION

2.1 Important Dosing Information

Evaluation of Iron Stores and Nutritional Factors

Evaluate the iron status in all patients before and during treatment. Administer supplemental iron therapy when serum ferritin is less than 100 mcg/L or when serum transferrin saturation is less than 20%. The majority of patients with CKD will require supplemental iron during the course of ESA therapy.

Monitoring of Response to Therapy

Correct or exclude other causes of anemia (e.g., vitamin deficiency, metabolic or chronic inflammatory conditions, bleeding, etc.) before initiating Mircera [see Warnings and Precautions (5.9)]. Following initiation of therapy and after each dose adjustment, monitor hemoglobin weekly until the hemoglobin level is stable and sufficient to minimize the need for RBC transfusion.

Individualization of Dosing

Individualize and use the lowest dose of Mircera sufficient to reduce the need for RBC transfusions [see Warnings and Precautions (5.1)]. In controlled trials, patients experienced greater risks for death, serious adverse cardiovascular reactions, and stroke when administered erythropoiesis-stimulating agents (ESAs) to target a hemoglobin level of greater than 11 g/dL for adult patients. No trial has identified a hemoglobin target level, ESA dose, or dosing strategy that does not increase these risks. Physicians and patients should weigh the possible benefits of decreasing transfusions against the increased risks of death and other serious cardiovascular adverse events [see Boxed Warning and Clinical Studies (14)].

2.2 For Adult Patients with CKD

Prefilled syringes are not designed for administration of partial doses. Round doses to the closest dose achievable with the prefilled syringes.

When initiating or adjusting therapy, monitor hemoglobin levels at least weekly until stable, then monitor at least monthly. When adjusting therapy consider hemoglobin rate of rise, rate of decline, ESA responsiveness and hemoglobin variability. A single hemoglobin excursion may not require a dosing change.

- Do not increase the dose more frequently than once every 4 weeks. Decreases in dose can occur more frequently. Avoid frequent dose adjustments.
- If the hemoglobin rises rapidly (e.g., more than 1 g/dL in any 2-week period), reduce the dose of Mircera by approximately 25% to the closest dose achievable with the prefilled syringes to reduce rapid responses.
- If the hemoglobin continues to rise following a dose reduction, discontinue Mircera until the hemoglobin level begins to decrease, at which point therapy should be restarted with a dose that is approximately 25% below the previously administered dose.
- For patients who do not respond adequately, if the hemoglobin has not increased by more than 1 g/dL after 4 weeks of therapy, increase the dose by approximately 25% to the closest dose achievable with the prefilled syringes.
- For patients who do not respond adequately over a 12-week escalation period, increasing the Mircera dose further is unlikely to improve response and may increase risks. Use the lowest dose that will maintain a hemoglobin level sufficient to reduce the need for RBC transfusions. Evaluate other causes of anemia. Discontinue Mircera if responsiveness does not improve.

Administer Mircera either intravenously or subcutaneously. When administered subcutaneously, Mircera should be injected in the abdomen, arm or thigh.

For Adult Patients with CKD on dialysis:

- Initiate Mircera treatment when the hemoglobin level is less than 10 g/dL.
- If the hemoglobin level approaches or exceeds 11 g/dL, reduce or interrupt the dose of Mircera.
- The recommended starting dose of Mircera for the treatment of anemia in adult CKD patients who are not currently treated with an ESA is 0.6 mcg/kg body weight administered once every two weeks as a single intravenous or subcutaneous injection. The intravenous route is recommended for patients receiving hemodialysis because the intravenous route may be less immunogenic [see Adverse Reactions (6.2)].
- Once the hemoglobin has been stabilized, Mircera may be administered once monthly using a dose that is twice that of the every-two-week dose and subsequently titrated as necessary.

For Adult Patients with CKD not on dialysis:

- Consider initiating Mircera treatment only when the hemoglobin level is less than 10 g/dL and the following considerations apply:
  - The rate of hemoglobin decline indicates the likelihood of requiring a RBC transfusion and,
  - Reducing the risk of alloimmunization and/or other RBC transfusion-related risks is a goal.
- If the hemoglobin level exceeds 10 g/dL, reduce or interrupt the dose of Mircera, and use the lowest dose of Mircera sufficient to reduce the need for RBC transfusions.
- The recommended starting dose of Mircera for the treatment of anemia in adult CKD patients who are not currently treated with an ESA is 1.2 mcg/kg body weight administered once every month as a single subcutaneous injection. Alternatively, a starting dose of 0.6 mcg/kg body weight may be administered once every two weeks as a single intravenous or subcutaneous injection.
- Once the hemoglobin has been stabilized, Mircera may be administered once monthly using a dose that is twice that of the every-two-week dose and subsequently titrated as necessary.

Refer patients who self-administer Mircera to the Instructions for Use [see Patient Counseling Information (17)].

Conversion from Epoetin alfa or Darbepoetin alfa to Mircera in Adult Patients with CKD

Mircera can be administered once every two weeks or once monthly to patients whose hemoglobin has been stabilized by treatment with an ESA (see Table 1). The dose of Mircera, given as a single intravenous or subcutaneous injection, should be based on the total weekly ESA dose at the time of conversion.

Table1: Mircera Starting Doses for Adult Patients Currently Receiving an ESA

Previous Weekly Epoetin alfa Dose (units/week) | Previous Weekly Darbepoetin alfa Dose (mcg/week) | Mircera Dose
Previous Weekly Epoetin alfa Dose (units/week) | Previous Weekly Darbepoetin alfa Dose (mcg/week) | Once Monthly (mcg/month) | Once Every Two Weeks (mcg/every two weeks)
Less than 8000 units | Less than 40 mcg | 120 mcg | 60 mcg
8000 units to 16000 units | 40 mcg to 80 mcg | 200 mcg | 100 mcg
More than 16000 units | More than 80 mcg | 360 mcg | 180 mcg

2.3 For Pediatric Patients with CKD

Conversion from Epoetin alfa or Darbepoetin alfa to Mircera in Pediatric Patients with CKD

Pre-filled syringes are not designed for administration of partial doses. Pediatric patients requiring a dose of less than 30 mcg of Mircera should not be treated with Mircera.

In patients less than 6 years of age, maintain the same route of administration as the previous ESA when switching from another ESA to Mircera.

Administer Mircera once every 4 weeks as an intravenous or subcutaneous injection to pediatric patients (ages 3 months to 17 years) whose hemoglobin level has been stabilized by treatment with an ESA. The starting dose of Mircera is calculated based on the total weekly ESA dose at the time of conversion. Refer to Table 2 for the dose of Mircera corresponding to the available commercial prefilled syringe strengths.

Table 2: Mircera Starting Doses for Pediatric Patients Currently Receiving an ESA

Previous Weekly Epoetin Alfa or Epoetin Beta Dose (Units/Week) | Previous Weekly Darbepoetin Alfa Dose (mcg/week) | Mircera Dose Once Every 4 Weeks (mcg)
Less than 1300 units | Less than 6 mcg | 30 mcg
1300 units to less than 2000 units | 6 mcg to less than 9 mcg | 50 mcg
2000 units to less than 2700 units | 9 mcg to less than 12 mcg | 75 mcg
2700 units to less than 3500 units | 12 mcg to less than 15 mcg | 100 mcg
3500 units to less than 4200 units | 15 mcg to less than 19 mcg | 120 mcg
4200 units to less than 5500 units | 19 mcg to less than 24 mcg | 150 mcg
5500 units to less than 7000 units | 24 mcg to less than 31 mcg | 200 mcg
7000 units to less than 9500 units | 31 mcg to less than 42 mcg | 250 mcg
greater than or equal to 9500 units | greater than or equal to 42 mcg | 360 mcg

In patients <less than 6 years of age, maintain the same route of administration as the previous ESA when switching from another ESA to Mircera.

If a dose adjustment is required to maintain the hemoglobin concentration above 10 g/dl and within the target range, refer to Table 3 for the Mircera dose adjustment based on hemoglobin response. Dose adjustments should not be made more often than once every 4 weeks.

Table 3: Mircera Dose Adjustments for Pediatric Patients

Hemoglobin Assessment | Compared with the Previous Mircera Dose
Hb decreases by more than 1.0 g/dL compared with baseline Hb | Increase dose by approximately 25% to the closest dose achievable with the prefilled syringes
Hb is less than 10 g/dL and greater than or equal to 9 g/dL (Hb<10.0 and ≥9.0 g/dL) | Increase dose by approximately 25% to the closest dose achievable with the prefilled syringes
Hb is less than 9 g/dL (Hb <9.0 g/dL) | Increase dose by approximately 50% to the closest dose achievable with the prefilled syringes
Hb increases by more than 1.0 g/dL compared with the baseline Hb | Decrease dose by approximately 25% to the closest dose achievable with the prefilled syringes
Hb is increasing and is approaching 12 g/dL or Hb is greater than or equal to 12 g/dL (Hb≥12 g/dL) | Decrease dose by approximately 25% to the closest dose achievable with the prefilled syringes
If Hb exceeds 12 g/dL and continues to increase following a dose reduction | Stop doses until Hb is less than 12.0 g/dL. Resume dose at approximately 25% below previous dose to the closest dose achievable with the prefilled syringes at next scheduled dosing day.

2.4 Preparation and Administration of Mircera

Mircera is packaged as single-dose prefilled syringes. Mircera contains no preservatives. Discard any unused portion. Do not pool unused portions from the prefilled syringes. Do not use the prefilled syringe more than once.

Always store Mircera prefilled syringes in their original cartons. Vigorous shaking or prolonged exposure to light should be avoided.

Do not mix Mircera with any parenteral solution.

Parenteral drug products should be inspected visually for particulate matter and discoloration prior to administration. Do not use any prefilled syringes exhibiting particulate matter or a coloration other than colorless to slightly yellowish.

For administration using the prefilled syringe, the plunger must be fully depressed during injection in order for the needle guard to activate. Following administration, remove the needle from the injection site and then release the plunger to allow the needle guard to move up until the entire needle is covered.

Children and adolescents less than 17 years of age should not self-inject Mircera. Intravenous and subcutaneous administration should be performed by a healthcare professional or adult caregiver.

See “Instructions for Use” for complete instructions on the preparation and administration of Mircera. Examine each prefilled syringe for the expiration date. Do not use Mircera after the expiration date.

3 DOSAGE FORMS AND STRENGTHS

Injection: 30 mcg, 50 mcg, 75 mcg, 100 mcg, 120 mcg, 150 mcg, 200 mcg, or 250 mcg in 0.3 mL clear, colorless to slightly yellowish solution in single-dose prefilled syringes

Injection: 360 mcg in 0.6 mL clear, colorless to slightly yellowish solution in single-dose prefilled syringes

4 CONTRAINDICATIONS

Mircera is contraindicated in patients with:

- Uncontrolled hypertension [see Warnings and Precautions (5.3)]
- Pure red cell aplasia (PRCA) that begins after treatment with Mircera or other erythropoietin protein drugs [see Warnings and Precautions (5.6)]
- History of serious or severe allergic reactions to Mircera (e.g., anaphylactic reactions, angioedema, bronchospasm, skin rash, and urticaria) [see Warnings and Precautions (5.7, 5.8)].

5 WARNINGS AND PRECAUTIONS

5.1 Increased Mortality, Myocardial Infarction, Stroke, and Thromboembolism

- In controlled clinical trials of patients with CKD comparing higher hemoglobin targets (13 to 14 g/dL) to lower targets (9 to 11.3 g/dL), ESAs increased the risk of death, myocardial infarction, stroke, congestive heart failure, thrombosis of hemodialysis vascular access, and other thromboembolic events in the higher target groups.
- Using ESAs to target a hemoglobin level of greater than 11 g/dL increases the risk of serious adverse cardiovascular reactions and has not been shown to provide additional benefit [see Clinical Studies (14)]. Use caution in patients with coexistent cardiovascular disease and stroke [see Dosage and Administration (2.2)]. Patients with CKD and an insufficient hemoglobin response to ESA therapy may be at even greater risk for cardiovascular reactions and mortality than other patients. A rate of hemoglobin rise of greater than 1 g/dL over 2 weeks may contribute to these risks.
- In controlled clinical trials of patients with cancer, ESAs increased the risks for death and serious adverse cardiovascular reactions. These adverse reactions included myocardial infarction and stroke.
- In controlled clinical trials, ESAs increased the risk of death in patients undergoing coronary artery bypass graft surgery (CABG) and the risk of deep venous thrombosis (DVT) in patients undergoing orthopedic procedures.

The design and overall results of the 3 large trials comparing higher and lower hemoglobin targets are shown in Table 4 (Normal Hematocrit Study (NHS), Correction of Hemoglobin Outcomes in Renal Insufficiency (CHOIR) and Trial to Reduce Cardiovascular Events with Aranesp® Therapy (TREAT)).

Table 4: Randomized Controlled Trials Showing Adverse Cardiovascular Outcomes in Patients With CKD

 | NHS (N = 1265) | CHOIR (N = 1432) | TREAT (N = 4038)
Time Period of Trial | 1993 to 1996 | 2003 to 2006 | 2004 to 2009
Population | CKD patients on hemodialysis with coexisting CHF or CAD, hematocrit 30 ± 3% on epoetin alfa | CKD patients not on dialysis with hemoglobin less than 11 g/dL not previously administered epoetin alfa | CKD patients not on dialysis with type II diabetes, hemoglobin ≤11 g/dL
Hemoglobin Target; Higher vs. Lower (g/dL) | 14.0 vs. 10.0 | 13.5 vs. 11.3 | 13.0 vs. ≥9.0
Median (Q1, Q3) Achieved Hemoglobin level (g/dL) | 12.6 (11.6, 13.3) vs. 10.3 (10.0, 10.7) | 13.0 (12.2, 13.4) vs. 11.4 (11.1, 11.6) | 12.5 (12.0, 12.8) vs. 10.6 (9.9, 11.3)
Primary Endpoint | All-cause mortality or nonfatal MI | All-cause mortality, MI, hospitalization for CHF, or stroke | All-cause mortality, MI, myocardial ischemia, heart failure, and stroke
Hazard Ratio or Relative Risk (95% CI) | 1.28 (1.06 to 1.56) | 1.34 (1.03 to 1.74) | 1.05 (0.94 to 1.17)
Adverse Outcome for Higher Target Group | All-cause mortality | All-cause mortality | Stroke
Hazard Ratio or Relative Risk (95% CI) | 1.27 (1.04 to 1.54) | 1.48 (0.97 to 2.27) | 1.92 (1.38 to 2.68)

Patients with Chronic Kidney Disease

NHS: A prospective, randomized, open-label study of 1265 patients with chronic kidney disease on dialysis with documented evidence of congestive heart failure or ischemic heart disease was designed to test the hypothesis that a higher target hematocrit (Hct) would result in improved outcomes compared with a lower target Hct. In this study, patients were randomized to epoetin alfa treatment targeted to a maintenance hemoglobin of either 14 ± 1 g/dL or 10 ± 1 g/dL. The trial was terminated early with adverse safety findings of higher mortality in the high hematocrit target group. Higher mortality (35% vs. 29%) was observed for the patients randomized to a target hemoglobin of 14 g/dL than for the patients randomized to a target hemoglobin of 10 g/dL. For all-cause mortality, the HR=1.27; 95% CI (1.04, 1.54); p=0.018. The incidence of nonfatal myocardial infarction, vascular access thrombosis, and other thrombotic events was also higher in the group randomized to a target hemoglobin of 14 g/dL.

CHOIR: In a randomized prospective trial, 1432 patients with anemia due to CKD who were not undergoing dialysis were assigned to epoetin alfa treatment targeting a maintenance hemoglobin concentration of 13.5 g/dL or 11.3 g/dL. The trial was terminated early with adverse safety findings. A major cardiovascular event (death, myocardial infarction, stroke, or hospitalization for congestive heart failure) occurred among 125 (18%) of the 715 patients in the higher hemoglobin group compared to 97 (14%) among the 717 patients in the lower hemoglobin group (HR 1.3, 95% CI: 1.0, 1.7 p=0.03).

TREAT: A randomized, double-blind, placebo-controlled, prospective trial of 4038 patients with: CKD not on dialysis (eGFR of 20 – 60 mL/min), anemia (hemoglobin levels ≤ 11 g/dL), and type 2 diabetes mellitus, patients were randomized to receive either darbepoetin alfa treatment or a matching placebo. Placebo group patients also received darbepoetin alfa when their hemoglobin levels were below 9 g/dL. The trial objectives were to demonstrate the benefit of darbepoetin alfa treatment of the anemia to a target hemoglobin level of 13 g/dL, when compared to a “placebo” group, by reducing the occurrence of either of two primary endpoints:
(1) a composite cardiovascular endpoint of all-cause mortality or a specified cardiovascular event (myocardial ischemia, CHF, MI, and CVA) or (2) a composite renal endpoint of all-cause mortality or progression to end stage renal disease. The overall risks for each of the two primary endpoints (the cardiovascular composite and the renal composite) were not reduced with darbepoetin alfa treatment (see Table 4), but the risk of stroke was increased nearly two-fold in the darbepoetin alfa-treated group vs. the placebo group: annualized stroke rate 2.1% vs. 1.1%, respectively, HR 1.92; 95% CI: 1.38, 2.68; p less than 0.001. The relative risk of stroke was particularly high in patients with a prior stroke: annualized stroke rate 5.2% in the darbepoetin alfa-treated group and 1.9% in the placebo group, HR 3.07; 95% CI: 1.44, 6.54. Also, among darbepoetin alfa-treated subjects with a past history of cancer, there were more deaths due to all causes and more deaths adjudicated as due to cancer, in comparison with the control group.

Patients with Cancer

An increased incidence of thromboembolic reactions, some serious and life-threatening, occurred in patients with cancer treated with ESAs.

In a randomized, placebo-controlled study (Study 1 in Table 5 [see Warnings and Precautions (5.2)]) of 939 women with metastatic breast cancer receiving chemotherapy, patients received either weekly epoetin alfa or placebo for up to a year. This study was designed to show that survival was superior when epoetin alfa was administered to prevent anemia (maintain hemoglobin levels between 12 and 14 g/dL or hematocrit between 36% and 42%). This study was terminated prematurely when interim results demonstrated a higher mortality at 4 months (8.7% vs. 3.4%) and a higher rate of fatal thrombotic reactions (1.1% vs. 0.2%) in the first 4 months of the study among patients treated with epoetin alfa. Based on Kaplan-Meier estimates, at the time of study termination, the 12-month survival was lower in the epoetin alfa group than in the placebo group (70% vs. 76%; HR 1.37, 95% CI: 1.07, 1.75; p = 0.012).

Patients Having Surgery

Mircera is not approved for reduction of RBC transfusions in patients scheduled for surgical procedures.

An increased incidence of deep vein thrombosis (DVT) in patients receiving epoetin alfa undergoing surgical orthopedic procedures has been observed. In a randomized controlled study (referred to as the “SPINE” study), 681 adult patients, not receiving prophylactic anticoagulation and undergoing spinal surgery, received epoetin alfa and standard of care (SOC) treatment, or SOC treatment alone. Preliminary analysis showed a higher incidence of DVT, determined by either Color Flow Duplex Imaging or by clinical symptoms, in the epoetin alfa group [16 patients (4.7%)] compared to the SOC group [7 patients (2.1%)]. In addition, 12 patients in the epoetin alfa group and 7 patients in the SOC group had other thrombotic vascular events.

Increased mortality was observed in a randomized placebo-controlled study of epoetin alfa in adult patients who were undergoing coronary artery bypass surgery (7 deaths in 126 patients randomized to epoetin alfa vs. no deaths among 56 patients receiving placebo). Four of these deaths occurred during the period of study drug administration and all four deaths were associated with thrombotic events.

5.2 Increased Mortality and/or Increased Risk of Tumor Progression or Recurrence in Patients with Cancer

Mircera is not indicated and is not recommended for use in the treatment of anemia due to cancer chemotherapy. A dose-ranging trial of Mircera in 153 patients who were undergoing chemotherapy for non-small cell lung cancer was terminated prematurely because more deaths occurred among patients receiving Mircera than another ESA.

ESAs resulted in decreased locoregional control/progression-free survival and/or overall survival (see Table 5). These findings were observed in studies of patients with advanced head and neck cancer receiving radiation therapy (Studies 5 and 6), in patients receiving chemotherapy for metastatic breast cancer (Study 1) or lymphoid malignancy (Study 2), and in patients with non-small cell lung cancer or various malignancies who were not receiving chemotherapy or radiotherapy (Studies 7 and 8).

Table 5: Randomized, Controlled Trials with Decreased Survival and/or Decreased Locoregional Control

Study/Tumor (n) | Hemoglobin Target | Achieved Hemoglobin (Median Q1,Q3*) | Primary Endpoint | Adverse Outcome for ESA-containing Arm
Chemotherapy
Cancer Study 1 Metastatic breast cancer (n=939) | 12 to 14 g/dL | 12.9 g/dL 12.2, 13.3 g/dL | 12-month overall survival | Decreased 12-month survival
Cancer Study 2 Lymphoid malignancy (n=344) | 13 to 15 g/dL (M) 13 to 14 g/dL (F) | 11.0 g/dL 9.8, 12.1 g/dL | Proportion of patients achieving a hemoglobin response | Decreased overall survival
Cancer Study 3 Early breast cancer (n=733) | 12.5 to 13 g/dL | 13.1 g/dL 12.5, 13.7 g/dL | Relapse-free and overall survival | Decreased 3-year relapse-free and overall survival
Cancer Study 4 Cervical cancer (n=114) | 12 to 14 g/dL | 12.7 g/dL 12.1, 13.3 g/dL | Progression-free and overall survival and locoregional control | Decreased 3-year progression-free and overall survival and locoregional control
Radiotherapy Alone
Cancer Study 5 Head and neck cancer (n=351) | more than 15 g/dL (M) more than 14 g/dL (F) | Not available | Locoregional progression-free survival (LRPFS) | Decreased 5-year locoregional progression-free survival Decreased overall survival
Cancer Study 6 Head and neck cancer (n=522) | 14 to 15.5 g/dL | Not available | Locoregional disease control (LRC) | Decreased locoregional disease control
No Chemotherapy or Radiotherapy
Cancer Study 7 Non-small cell lung cancer (n=70) | 12 to 14 g/dL | Not available | Quality of life | Decreased overall survival
Cancer Study 8 Non-myeloid malignancy (n=989) | 12 to 13 g/dL | 10.6 g/dL 9.4, 11.8 g/dL | RBC transfusions | Decreased overall survival
*Q1= 25th percentile; Q3= 75th percentile

Decreased Overall Survival

Cancer Study 1 (the “BEST” study) was previously described [see Warnings and Precautions (5.1)]. Mortality at 4 months (8.7% vs. 3.4%) was significantly higher in the epoetin alfa arm. The most common investigator-attributed cause of death within the first 4 months was disease progression; 28 of 41 deaths in the epoetin alfa arm and 13 of 16 deaths in the placebo arm were attributed to disease progression. Investigator assessed time to tumor progression was not different between the two groups. Survival at 12 months was significantly lower in the epoetin alfa arm (70% vs. 76%, HR 1.37, 95% CI: 1.07, 1.75; p=0.012).

Cancer Study 2 was a Phase 3, double-blind, randomized (darbepoetin alfa vs. placebo) study conducted in 344 anemic patients with lymphoid malignancy receiving chemotherapy. With a median follow-up of 29 months, overall mortality rates were significantly higher among patients randomized to darbepoetin alfa as compared to placebo (HR 1.36, 95% CI: 1.02, 1.82).

Cancer Study 7 was a Phase 3, multicenter, randomized (epoetin alfa vs. placebo), double-blind study, in which patients with advanced non-small cell lung cancer receiving only palliative radiotherapy or no active therapy were treated with epoetin alfa to achieve and maintain hemoglobin levels between 12 and 14 g/dL. Following an interim analysis of 70 of 300 patients planned, a significant difference in survival in favor of the patients on the placebo arm of the trial was observed (median survival 63 vs. 129 days; HR 1.84; p=0.04).

Cancer Study 8 was a Phase 3, double-blind, randomized (darbepoetin alfa vs. placebo), 16-week study in 989 anemic patients with active malignant disease, neither receiving nor planning to receive chemotherapy or radiation therapy. There was no evidence of a statistically significant reduction in proportion of patients receiving RBC transfusions. The median survival was shorter in the darbepoetin alfa treatment group (8 months) compared with the placebo group (10.8 months); HR 1.30, 95% CI: 1.07, 1.57.

Decreased Progression-Free Survival and Overall Survival

Cancer Study 3 (the “PREPARE” study) was a randomized controlled study in which darbepoetin alfa was administered to prevent anemia conducted in 733 women receiving neo-adjuvant breast cancer treatment. A final analysis was performed after a median follow-up of approximately 3 years at which time the survival rate was lower (86% vs. 90%, HR 1.42, 95% CI: 0.93, 2.18) and relapse-free survival rate was lower (72% vs. 78%, HR 1.33, 95% CI: 0.99, 1.79) in the darbepoetin alfa-treated arm compared to the control arm.

Cancer Study 4 (protocol GOG 191) was a randomized controlled study that enrolled 114 of a planned 460 cervical cancer patients receiving chemotherapy and radiotherapy. Patients were randomized to receive epoetin alfa to maintain hemoglobin between 12 and 14 g/dL or to transfusion support as needed. The study was terminated prematurely due to an increase in thromboembolic events in epoetin alfa-treated patients compared to control (19% vs. 9%). Both local recurrence (21% vs. 20%) and distant recurrence (12% vs. 7%) were more frequent in epoetin alfa-treated patients compared to control. Progression-free survival at 3 years was lower in the epoetin alfa-treated group compared to control (59% vs. 62%, HR 1.06, 95% CI: 0.58, 1.91). Overall survival at 3 years was lower in the epoetin alfa-treated group compared to control (61% vs. 71%, HR 1.28, 95% CI: 0.68, 2.42).

Cancer Study 5 (the “ENHANCE” study) was a randomized controlled study in 351 head and neck cancer patients where epoetin beta or placebo was administered to achieve target hemoglobins of 14 and 15 g/dL for women and men, respectively. Locoregional progression-free survival was significantly shorter in patients receiving epoetin beta (HR 1.62, 95% CI: 1.22, 2.14, p=0.0008) with a median of 406 days epoetin beta vs. 745 days placebo. Overall survival was significantly shorter in patients receiving epoetin beta (HR 1.39, 95% CI: 1.05, 1.84; p=0.02).

Decreased Locoregional Control

Cancer Study 6 (DAHANCA 10) was conducted in 522 patients with primary squamous cell carcinoma of the head and neck receiving radiation therapy randomized to darbepoetin alfa with radiotherapy or radiotherapy alone. An interim analysis on 484 patients demonstrated that locoregional control at 5 years was significantly shorter in patients receiving darbepoetin alfa (RR 1.44, 95% CI: 1.06, 1.96; p=0.02). Overall survival was shorter in patients receiving darbepoetin alfa (RR 1.28, 95% CI: 0.98, 1.68; p=0.08).

5.3 Hypertension

Mircera is contraindicated in patients with uncontrolled hypertension.

In Mircera clinical studies, approximately 27% of patients with CKD, including patients on dialysis and patients not on dialysis, required intensification of antihypertensive therapy. Hypertensive encephalopathy and/or seizures have been observed in patients with CKD treated with Mircera [see Warnings and Precautions (5.4)].

Appropriately control hypertension prior to initiation of and during treatment with Mircera. Reduce or withhold Mircera if blood pressure becomes difficult to control. Advise patients of the importance of compliance with antihypertensive therapy and dietary restrictions [see Patient Counseling Information (17)].

5.4 Seizures

Seizures have occurred in patients participating in Mircera clinical studies. During the first several months following initiation of Mircera, monitor patients closely for premonitory neurologic symptoms. Advise patients to contact their healthcare practitioner for new-onset seizures, premonitory symptoms, or change in seizure frequency.

5.5 Lack or Loss of Hemoglobin Response to Mircera

For lack or loss of hemoglobin response to Mircera, initiate a search for causative factors (e.g., iron deficiency, infection, inflammation, bleeding).

If typical causes of lack or loss of hemoglobin response are excluded, evaluate for PRCA [see Warnings and Precautions (5.6)]. In the absence of PRCA, follow dosing recommendations for management of patients with an insufficient response to Mircera therapy [see Dosage and Administration (2.1)].

5.6 Pure Red Cell Aplasia

Cases of PRCA and of severe anemia, with or without other cytopenias that arise following the development of neutralizing antibodies to erythropoietin have been reported in the postmarketing setting in patients treated with Mircera. This has been reported predominantly in patients with CKD receiving ESAs by subcutaneous administration. PRCA was not observed in clinical studies of Mircera.

PRCA has also been reported in patients receiving ESAs for anemia related to hepatitis C treatment (an indication for which Mircera is not approved).

If severe anemia and low reticulocyte count develop during treatment with Mircera, withhold Mircera and evaluate patients for neutralizing antibodies to erythropoietin [see Warnings and Precautions (5.5)]. Serum samples should be obtained at least a month after the last Mircera administration to prevent interference of Mircera with the assay. Contact Vifor at 1-800-576-8295 to perform assays for binding and neutralizing antibodies. Permanently discontinue Mircera in patients who develop PRCA following treatment with Mircera or other erythropoietin protein drugs. Do not switch patients to other ESAs as antibodies may cross-react [see Adverse Reactions (6.2)].

5.7 Serious Allergic Reactions

Serious allergic reactions, including anaphylactic reactions, angioedema, bronchospasm, tachycardia, pruritus skin rash and urticaria have been reported in patients treated with Mircera. If a serious allergic or anaphylactic reaction occurs due to Mircera, immediately and permanently discontinue Mircera and administer appropriate therapy.

5.8 Severe Cutaneous Reactions

Blistering and skin exfoliation reactions including Erythema multiforme and Stevens-Johnson Syndrome (SJS)/Toxic Epidermal Necrolysis (TEN), have been reported in patients treated with ESAs (including Mircera) in the postmarketing setting. Discontinue Mircera therapy immediately if a severe cutaneous reaction, such as SJS/TEN, is suspected.

5.9 Dialysis Management

Patients may require adjustments in their dialysis prescription after initiation of Mircera. Patients receiving Mircera may require increased anticoagulation with heparin to prevent clotting of the extracorporeal circuit during hemodialysis.

6 ADVERSE REACTIONS

The following serious adverse reactions are discussed in greater detail in other sections of the labeling:

- Increased Mortality, Myocardial Infarction, Stroke, and Thromboembolism [see Warnings and Precautions (5.1)]
- Increased Mortality and/or Tumor Progression in Patients with Cancer [see Warnings and Precautions (5.2)]
- Hypertension [see Warnings and Precautions (5.3)]
- Seizures [see Warnings and Precautions (5.4)]
- Pure Red Cell Aplasia [see Warnings and Precautions (5.6)]
- Serious Allergic Reactions [see Warnings and Precautions (5.7)]
- Severe Cutaneous Reactions [see Warnings and Precautions (5.8)]

6.1 Clinical Trials Experience

Because clinical trials are conducted under widely varying conditions, adverse reaction rates observed in the clinical studies of Mircera cannot be directly compared to rates in the clinical trials of other drugs and may not reflect the rates observed in practice.

Adult Patients

The data described below reflect exposure to Mircera in 2737 patients, including 1451 exposed for 6 months and 1144 exposed for greater than one year. Mircera was studied primarily in active-controlled studies (n=1789 received Mircera, and n=948 received another ESA) and in long-term follow up studies. The population was 18 to 92 years of age, 58% male, and the percentage of Caucasian, Black (including African Americans), Asian and Hispanic patients were 73%, 20%, 5%, and 9%, respectively. Approximately 85% of the patients were receiving dialysis. Most patients received Mircera using dosing regimens of once every two or four weeks, administered subcutaneously or intravenously.

The most commonly reported adverse reactions in ≥10% of patients were hypertension [see Warnings and Precautions (5.3)], diarrhea, and nasopharyngitis. The most common adverse reactions that led to treatment discontinuation in the Mircera clinical studies were: hypertension, coronary artery disease, anemia, concomitant termination of other CKD therapy and septic shock. Some of the adverse reactions reported are typically associated with CKD, or recognized complications of dialysis, and may not necessarily be attributable to Mircera therapy. Adverse reaction rates did not importantly differ between patients receiving Mircera or another ESA.

Table 6 summarizes the most frequent adverse reactions (≥5%) in patients treated with Mircera.

Table 6: Adverse Reactions Occurring in ≥ 5% of CKD Patients

BODY SYSTEM Adverse Reaction | Patients Treated with Mircera (n=1789)
VASCULAR
Hypertension | 13%
Hypotension | 5%
GASTROINTESTINAL
Diarrhea | 11%
Vomiting | 6%
Constipation | 5%
INFECTIONS AND INFESTATIONS
Nasopharyngitis | 11%
Upper Respiratory Tract Infection | 9%
Urinary Tract Infection | 5%
NERVOUS SYSTEM
Headache | 9%
MUSCULOSKELETAL AND CONNECTIVE TISSUE
Muscle Spasms | 8%
Back Pain | 6%
Pain in Extremity | 5%
INJURY, POISONING AND PROCEDURAL COMPLICATIONS
Procedural Hypotension | 8%
Arteriovenous Fistula Thrombosis | 5%
Arteriovenous Fistula Site Complication | 5%
METABOLISM AND NUTRITION
Fluid Overload | 7%
RESPIRATORY, THORACIC AND MEDIASTINAL
Cough | 6%

In the controlled trials, the rates of serious adverse reactions did not importantly differ between patients receiving Mircera and another ESA (38% vs. 42%) except for the occurrence of serious gastrointestinal hemorrhage (1.2% vs. 0.2%). Serious hemorrhagic adverse reactions of all types occurred among 5% and 4% of patients receiving Mircera or another ESA, respectively.

Pediatric Patients

In an open-label, multiple dose study, 64 pediatric patients (ages 5 to 17 years) with CKD who were on hemodialysis and who had stable hemoglobin levels while previously receiving another ESA (epoetin alfa/beta or darbepoetin alfa) were then converted to Mircera administered intravenously once every 4 weeks for 20 weeks (core study period). Patients who completed the core study period with hemoglobin within ± 1 g/dL of their baseline hemoglobin and within the target range of 10 to 12 g/dL were eligible to enter an optional 52-week safety extension period (total duration of treatment, up to 73 weeks). In the extension period, 25 (out of 37) patients were treated for at least an additional 5 months. During the whole study (core study and safety extension), 33 patients were exposed to Mircera for at least 6 months and 19 were exposed for greater than 15 months.

All reported adverse reactions regardless of causality (more than 5% incidence) in the pediatric population included headache (22%), nasopharyngitis (22%), hypertension (19%), vomiting (11%), bronchitis (9%), abdominal pain (8%), arteriovenous fistula thrombosis (6%), cough (6%), device related infection (6%), hyperkalemia (6%), pharyngitis (6%), pyrexia (6%), thrombocytopenia (6%), and thrombosis in device (6%).

A second open-label, single-arm, multicenter study was conducted to ascertain the optimal starting dose of Mircera given subcutaneously for the maintenance treatment of anemia in 40 pediatric patients (ages 3 months to 17 years) with CKD on dialysis or not on dialysis. Patients completing the 20 weeks of treatment (core period) with Hb within ±1 g/dL of their baseline Hb and within the target range of 10 to 12 g/dL, were eligible to enter an optional 24-week safety extension period. Mircera was administered subcutaneously once every 4 weeks for the duration of the study. Thirty-eight (38) patients were exposed to Mircera for 20 weeks, and 21 patients were exposed to Mircera for 44 weeks. Overall, the pattern of adverse events reported was similar to the established safety profile of Mircera in adult patients and the patients aged 5 to 17 years in the previous intravenous study.

6.2 Postmarketing Experience

The following adverse reactions have been identified during post-approval use of Mircera. Because these reactions are reported voluntarily from a population of uncertain size, it is not always possible to reliably estimate their frequency or establish a causal relationship to drug exposure.

Hypersensitivity

Stevens-Johnson syndrome/toxic epidermal necrolysis has been reported [see Warnings and Precautions (5.7)].

Pure Red Cell Aplasia (PRCA)

Cases of PRCA and of severe anemia, with or without other cytopenias that arise following the development of neutralizing antibodies to erythropoietin have been reported in patients treated with Mircera [see Warnings and Precautions (5.6)].

8 USE IN SPECIFIC POPULATIONS

8.1 Pregnancy

Risk Summary

Available data from a small number of published case reports and postmarketing experience with Mircera use in pregnancy are insufficient to identify a drug associated risk of major birth defects, miscarriage, or adverse maternal or fetal outcomes. Chronic kidney disease is associated with maternal and embryo-fetal risks (see Clinical Considerations). In animal reproduction studies, administration of methoxy polyethylene glycol-epoetin beta to rats and rabbits during pregnancy and lactation adversely affected offspring at doses 17-fold and greater than the recommended human dose (see Data).

The estimated background risk of major birth defects and miscarriage for the indicated population is unknown. All pregnancies have a background risk of birth defect, loss, or other adverse outcomes. In the U.S. general population, the estimated background risks of major birth defects and miscarriage in clinically recognized pregnancies is 2 to 4% and 15 to 20%, respectively.

Clinical Considerations

Disease Associated Maternal and/or Embryo-Fetal Risk

Pregnancy in women with chronic kidney disease has been associated with adverse outcomes including hypertension, pre-eclampsia, miscarriage, premature birth, low-birth-weight, polyhydramnios, and intrauterine growth restriction.

Data

When methoxy polyethylene glycol-epoetin beta was administered subcutaneously to rats and rabbits during gestation (including the period of organogenesis), bone malformation was observed in both species at 50 mcg/kg once every three days (corresponding to 500 mcg/kg/month or 417-fold the recommended human dose) in studies of embryo-fetal development. This effect was observed as missing caudal vertebrae resulting in a thread-like tail in one rat fetus, absent first digit metacarpal and phalanx on each forelimb resulting in absent pollex in one rabbit fetus, and fused fourth and fifth cervical vertebrae centra in another rabbit fetus. Dose-related reduction in fetal weights was observed in both rats and rabbits. At doses 5 mcg/kg once every three days and higher, corresponding to 50 mcg/kg/month or 42-fold the recommended human dose, methoxy polyethylene glycol-epoetin beta caused exaggerated pharmacodynamic effects in dams.

Once-weekly doses of methoxy polyethylene glycol-epoetin beta up to 50 mcg/kg/dose (corresponding to 200 mcg/kg/month or 167-fold the recommended human dose) given to pregnant and lactating rats did not adversely affect pregnancy parameters, natural delivery or litter observations in a study of pre-and postnatal development. Increased deaths and significant reduction in the growth rate of the F1 generation were observed during lactation and early post weaning period at 20 and 50 mcg/kg/dose, corresponding to 80 and 200 mcg/kg/month or 67- and 167-fold the recommended human dose. A significant reduction in the growth rate of the F1 generation was evident already at 5 mcg/kg/dose, corresponding to 20 mcg/kg/month or 17-fold the recommended human dose. However, no remarkable effect on reflex, physical and cognitive development or reproductive performance was observed in F1 generation of any dose groups.

The dose level not causing any adverse effect on dams or offspring was not determined.

8.2 Lactation

Risk Summary

There are no data on the presence of methoxy polyethylene glycol-epoetin beta in human milk, the effects on the breastfed child, or the effects on milk production. However, endogenous erythropoietin is present in human milk. In rats, methoxy polyethylene glycol-epoetin beta was present in maternal milk (see Data). When a drug is present in animal milk, it is likely that the drug will be present in human milk. The lack of clinical data during lactation precludes a clear determination of the risk of Mircera to a child during lactation. Therefore, the developmental and health benefits of breastfeeding should be considered along with the mother’s clinical need for Mircera and any potential adverse effects on the breastfed child from Mircera or from the underlying maternal condition.

Data

A dose of methoxy polyethylene glycol-epoetin beta approximately 3-fold greater than the recommended human dose was administered to lactating rats. Methoxy polyethylene glycol-epoetin beta was detected in maternal milk 4 hours postdose and reached maximum concentration 48 hours postdose. The maximum amount of methoxy polyethylene glycol-epoetin beta in milk was about 10-fold lower than in serum. The concentration of drug in animal milk does not necessarily predict the concentration of drug in human milk.

8.4 Pediatric Use

The safety and effectiveness of intravenous and subcutaneous Mircera for the treatment of anemia due to CKD have been established in pediatric patients 3 months to 17 years of age on dialysis and not on dialysis who are converting from another ESA after their hemoglobin level was stabilized with an ESA. The use of Mircera in this pediatric age group is supported by evidence from adequate and well-controlled studies of Mircera in adults, a dose-finding study in 64 pediatric patients 5 to 17 years of age with CKD on hemodialysis and a subcutaneous dose-finding study in 40 patients 3 months to 17 years of age with CKD on dialysis or not on dialysis. The adverse reaction profile observed in pediatric patients was consistent with the safety profile found in adults. The safety and effectiveness of Mircera have not been established in patients less than 3 months of age [see Adverse Reactions (6.1) and Clinical Studies (14.2)].

The safety and effectiveness of Mircera have not been established for treatment of anemia in pediatric patients whose hemoglobin level has not been previously stabilized by treatment with an ESA.

8.5 Geriatric Use

Clinical studies of Mircera did not include sufficient numbers of subjects aged 65 and over to determine whether they respond differently from younger subjects. Other reported clinical experience has not identified differences in responses between the elderly and younger patients. In general, dose selection for an elderly patient should be cautious, usually starting at the low end of the dosing range, reflecting the greater frequency of decreased hepatic, renal, or cardiac function and of concomitant disease or other drug therapy.

9 DRUG ABUSE AND DEPENDENCE

9.1 Controlled Substance

Mircera contains methoxy polyethylene glycol-epoetin beta which is not a controlled substance.

9.2 Abuse

Abuse is the intentional, non-therapeutic use of a drug, even once, for its desirable psychological or physiological effects. Abuse of Mircera may be seen in athletes for the effects on erythropoiesis. Abuse of drugs that increase erythropoiesis, such as Mircera, by healthy persons may lead to life-threatening cardiovascular complications (e.g., stroke, myocardial infarction, and thromboembolism).

In animal studies, methoxy polyethylene glycol-epoetin beta showed low distribution into the CNS which did not cause behavioral effects consistent with CNS activity.

10 OVERDOSAGE

Mircera overdosage can elevate hemoglobin levels above the desired level, which should be managed with discontinuation or reduction of Mircera dosage and/or with phlebotomy, as clinically indicated [see Pharmacodynamics (12.2)]. Cases of severe hypertension have been observed following overdose with ESAs [see Warnings and Precautions (5.3)].

11 DESCRIPTION

Methoxy polyethylene glycol-epoetin beta, is an ESA which differs from erythropoietin through formation of a chemical bond between either the N-terminal amino group or the ε-amino group of any lysine present in erythropoietin, predominantly Lys^52 and Lys^45, and methoxy polyethylene glycol (PEG) butanoic acid (approximately 30,000 daltons). This results in a total molecular weight of approximately 60,000 daltons. Methoxy polyethylene glycol-epoetin beta is produced in Chinese hamster ovary (CHO) cells using recombinant DNA technology.

Mircera is formulated as a sterile, preservative-free protein solution for intravenous or subcutaneous administration. Mircera (methoxy polyethylene glycol-epoetin beta) injection is supplied in prefilled syringes (30 mcg, 50 mcg, 75 mcg, 100 mcg, 120 mcg, 150 mcg, 200 mcg, or 250 mcg in 0.3 mL) and formulated in an aqueous solution containing mannitol (9 mg), methionine (0.447 mg), poloxamer 188 (0.03 mg), sodium phosphate monobasic monohydrate (0.414 mg), and sodium sulfate (1.704 mg). Mircera 360 mcg in 0.6 mL is formulated in an aqueous solution containing mannitol (18 mg), methionine (0.894 mg), poloxamer 188 (0.06 mg), sodium phosphate monobasic monohydrate (0.828 mg), and sodium sulfate (3.408 mg). The solution is clear, colorless to slightly yellowish and the pH is 6.2 ± 0.2.

12 CLINICAL PHARMACOLOGY

12.1 Mechanism of Action

Mircera is an erythropoietin receptor activator with greater activity in vivo as well as increased half-life, in contrast to erythropoietin. A primary growth factor for erythroid development, erythropoietin is produced in the kidney and released into the bloodstream in response to hypoxia. In responding to hypoxia, erythropoietin interacts with erythroid progenitor cells to increase red cell production. Production of endogenous erythropoietin is impaired in patients with CKD and erythropoietin deficiency is the primary cause of their anemia.

12.2 Pharmacodynamics

Following a single-dose of Mircera in adult patients with CKD, the onset of hemoglobin increase (defined as an increase more than 0.4 g/dL from baseline) was observed 7 to 15 days following initial dose administration [see Dosage and Administration (2.2)].

12.3 Pharmacokinetics

The pharmacokinetics of methoxy polyethylene glycol-epoetin beta were studied in adult anemic patients with CKD including patients on dialysis and those not on dialysis. Parameters are presented as the geometric mean [% coefficient of variation (%CV)] unless otherwise specified.

Methoxy polyethylene glycol-epoetin beta did not accumulate following administration every four weeks. However, when Mircera was administered every 2 weeks, serum concentrations at steady state increased by 12%. Multiple dosing had no effect on clearance, volume of distribution or bioavailability of methoxy polyethylene glycol-epoetin beta.

Absorption

Following the subcutaneous administration of Mircera, the maximum serum concentrations of methoxy polyethylene glycol-epoetin beta were observed at a median [min, max] time of 72 [24, 192] hours. The absolute bioavailability of Mircera after the subcutaneous administration was 62%.

Distribution

The volume of distribution at steady state was 61 [46%] mL/kg.

Elimination

Following an intravenous administration of Mircera 0.4 mcg/kg body weight to patients with CKD receiving peritoneal dialysis, the observed terminal half-life was 119 [55%] hours, and the total systemic clearance was 0.47 [35%] mL/hr/kg. Following a subcutaneous administration of Mircera 0.8 mcg/kg to CKD patients receiving peritoneal dialysis, the terminal half-life was 124 [57%] hours.

Specific Populations

The pharmacokinetics of methoxy polyethylene glycol-epoetin beta were not altered by age (range: 6-89 years), gender, race, severe hepatic impairment (Child-Pugh Class C), site of subcutaneous injection (abdomen, arm or thigh), or the use of dialysis.

Pediatric Patients

A population pharmacokinetic analysis was performed with data from 103 pediatric patients ages 6 months to 17 years and 524 adult patients. Pediatric patients received Mircera intravenously (N=63, all on hemodialysis) or subcutaneously (total N=40, n=17 on pre-dialysis, n=18 on peritoneal dialysis and n=5 on hemodialysis). The covariate analysis showed a positive body weight effect on clearance (CL) and volume of distribution (V), and a positive age effect on V. Once those covariate effects were taken into account together with the addition of a pediatric subcutaneous bioavailability of 67%, compared to 31% in adults, no differences could be observed in the pharmacokinetic properties of Mircera in pediatric patients compared to adult patients.

12.6 Immunogenicity

The observed incidence of anti-drug antibodies is highly dependent on the sensitivity and specificity of the assay. Differences in assay methods preclude meaningful comparisons of the incidence of anti-drug antibodies in the studies described below with the incidence of anti-drug antibodies in other studies, including those of Mircera or of other methoxy polyethylene glycol-epoetin beta products.

Neutralizing antibodies to Mircera that cross-react with endogenous erythropoietin and other ESAs can result in PRCA or severe anemia (with or without other cytopenias) [see Warnings and Precautions (5.6)]. Compared to subcutaneous administration, the intravenous route of administration may lessen the risk for development of antibodies to Mircera.

In 1789 patients treated with Mircera in clinical studies, antibody testing using an enzyme-linked immunosorbent assay (ELISA) was conducted at baseline and during treatment. Antibody development was not detected in any of the patients. ELISA testing was conducted in 104 pediatric patients. In the first study (NCT00717366), blood samples to measure anti-Mircera and anti-EPO antibodies were collected on Week 1, Week 13, Week 21 and Week 73. In the second study (NCT03552393), they were measured at Week 1, Week 9, Week 21, and Week 45. No patients tested positive at any time during the first study. In the second study, two patients tested positive for anti-Mircera and anti-EPO antibodies. For one patient, the Week 1 samples before the first Mircera administration were already positive. The second patient had a transient positive test at Week 21. The transient presence of antibodies did not neutralize the response and was not associated with any adverse events.

Because of the low occurrence of anti-drug antibodies, the effect of these antibodies on the pharmacokinetics, pharmacodynamics, safety, and/or effectiveness of methoxy polyethylene glycol-epoetin beta products is unknown.

13 NONCLINICAL TOXICOLOGY

13.1 Carcinogenesis, Mutagenesis, Impairment of Fertility

No carcinogenicity or genotoxicity studies have been conducted with Mircera. Methoxy polyethylene glycol-epoetin beta did not induce a proliferative response in either the erythropoietin receptor positive cell lines HepG2 and K562 or the erythropoietin receptor negative cell line RT112 in vitro. In addition, using a panel of human tissues, the in vitro binding of methoxy polyethylene glycol-epoetin beta was observed only in bone marrow progenitor cells.

When methoxy polyethylene glycol-epoetin beta was administered subcutaneously to male and female rats prior to and during mating, reproductive performance, fertility, and sperm assessment parameters were not affected.

14 CLINICAL STUDIES

14.1 Adult Patients

Patients with Chronic Kidney Disease on Dialysis: ESA Effects on Rates of Transfusion

In early clinical studies conducted in CKD patients on dialysis, ESAs have been shown to reduce the use of RBC transfusions. These studies enrolled patients with mean baseline hemoglobin levels of approximately 7.5 g/dL and ESAs were generally titrated to achieve a hemoglobin level of approximately 12 g/dL. Fewer transfusions were given during the ESA treatment period when compared to a pre-treatment interval.

In NHS, the yearly transfusion rate was 51.5% in the lower hemoglobin group (10 g/dL) and 32.4% in the higher hemoglobin group (14 g/dL).

Patients with Chronic Kidney Disease Not on Dialysis: ESA Effects on Rates of Transfusion

In TREAT, a randomized, double-blind trial of 4038 patients with CKD and type 2 diabetes not on dialysis, a post-hoc analysis showed that the proportion of patients receiving RBC transfusions was lower in patients administered an ESA to target a hemoglobin of 13 g/dL compared to the control arm in which the ESA was administered intermittently if hemoglobin concentration decreased to less than 9 g/dL (15% vs. 25%, respectively). In CHOIR, a randomized open-label study of 1432 patients with CKD not on dialysis, use of an ESA to target a higher (13.5 g/dL) vs. lower (11.3 g/dL) hemoglobin goal did not reduce the use of RBC transfusions. In each trial, no benefits occurred for the cardiovascular or end-stage renal disease outcomes. In each trial, the potential benefit of ESA therapy was offset by worse cardiovascular safety outcomes resulting in an unfavorable benefit-risk profile [see Warnings and Precautions (5.1)].

ESA Effects on Quality of Life

Mircera use has not been demonstrated in controlled clinical trials to improve quality of life, fatigue, or patient well-being.

ESA Effects on Rates of Death and Other Serious Cardiac Adverse Events

Three randomized outcome trials (NHS, CHOIR and TREAT) have been conducted in patients with CKD using Epogen/PROCRIT/Aranesp to target higher vs. lower hemoglobin levels. Though these trials were designed to establish a cardiovascular or renal benefit of targeting higher hemoglobin levels, in all 3 studies, patients randomized to the higher hemoglobin target experienced worse cardiovascular outcomes and showed no reduction in progression to ESRD. In each trial, the potential benefit of ESA therapy was offset by worse cardiovascular safety outcomes resulting in an unfavorable benefit-risk profile [see Warnings and Precautions (5.1)].

Other ESA Trials

The efficacy and safety of Mircera were assessed in six open-label, multi-center clinical studies that randomized patients to either Mircera or a comparator ESA. Two studies evaluated anemic patients with CKD who were not treated with an ESA at baseline and four studies evaluated patients who were receiving an ESA for treatment of the anemia of CKD. In all studies, patients were assessed as clinically stable at baseline and without evidence of infection or inflammation as determined by history and laboratory data, including C-reactive protein (CRP ≤ 15 mg/L for study 1 and CRP ≤ 30 mg/L for studies 2 to 6). A CRP value above the threshold led to the exclusion of no more than 3% of the screened patients.

In the clinical studies, ESAs were administered to achieve specific hemoglobin levels (see Table 7 and Table 8). Following stabilization of hemoglobin levels (12 g/dL), the median monthly Mircera dose was 150 mcg (range of 97 mcg to 270 mcg).

Patients Not Currently Treated with an ESA

In Study 1 patients who were not receiving dialysis were randomized to Mircera or darbepoetin alfa, administered for 28 weeks. The starting dose of Mircera was 0.6 mcg/kg administered subcutaneously once every two weeks and the starting dose of darbepoetin alfa was 0.45 mcg/kg administered subcutaneously once a week. In Study 2, patients who were receiving dialysis were randomized to Mircera or another ESA (epoetin alfa or epoetin beta), administered for 24 weeks. The starting dose of Mircera was 0.4 mcg/kg administered intravenously once every two weeks and the starting dose of the comparator was administered intravenously three times a week, consistent with the product’s recommended dose. In these studies, the observed median dose of Mircera once every two weeks over the course of the correction/evaluation period was 0.6 mcg/kg. Table 7 provides the results of the two studies.

Table 7: Clinical Studies in Patients Not Currently Treated with an ESA

Group (n) | Percent Achieving Goal* (95% CI) | Mean Hemoglobin Change from Baseline (g/dL) | RBC Transfusion, %
Study 1
Mircera (n=162) | 98 (94, 99) | 2.1 | 2.5
Darbepoetin alfa (n=162) | 96 (92, 99) | 2.0 | 6.8
Study 2
Mircera (n=135) | 93 (88, 97) | 2.7 | 5.2
Epoetin alfa/beta (n=46) | 91 (79, 98) | 2.6 | 4.3
*Goal: hemoglobin increase of at least 1 g/dL and to a level of at least 11 g/dL without RBC transfusion; hemoglobin levels were to be maintained within the range of 11 to 13 g/dL.

In the CORDATUS trial (NCT00559273), a randomized controlled study in patients with CKD not on dialysis and not currently treated with an ESA, Mircera, administered once monthly, was compared to darbepoetin alfa administered every week or every two weeks. Both treatment groups achieved statistical significance for hemoglobin response rate comparing with a fixed response rate of 60% [Mircera: 94%, CI: (89%, 97%), p<0.0001; darbepoetin alfa: 94%, CI: (88%, 97%), p<0.0001]. The Mircera group also achieved non-inferiority to the darbepoetin alfa group on the mean change of the baseline-adjusted Hb based on the protocol-specified NI margin of -0.75 [Mircera: 1.62 g/dL; darbepoetin alfa: 1.66 g/dL; difference: -0.036 g/dL with a two-sided 95% CI: (-0.252, 0.180)].

Patients Currently Treated with an ESA

Four studies assessed the ability of Mircera to maintain hemoglobin levels among patients currently treated with other ESAs. Patients were randomized to receive Mircera administrations either once every two weeks or once every four weeks, or to continue their current ESA dose and schedule. The initial Mircera dose was determined based on the patient’s previous weekly ESA dose. As shown in Table 8, treatment with Mircera once every two weeks and once every four weeks maintained hemoglobin levels within the targeted hemoglobin range (10 to 13.5 g/dL).

Table 8: Clinical Studies in Patients Currently Treated with an ESA

Group (n) | Mean Baseline Hemoglobin | Evaluation Period Hemoglobin (Mean) | Between-group Difference*, g/dL (95% or 97.5% CI)
Study 3
Mircera intravenously every 2 weeks (n=223) | 12.0 | 11.9 | 0.0 (−0.2, 0.2)
Mircera intravenously every 4 weeks (n=224) | 11.9 | 11.9 | 0.1 (−0.2, 0.3)
Epoetin alfa/beta intravenously (n=226) | 12.0 | 11.9 | n/a
Study 4
Mircera subcutaneously every 2 weeks (n=190) | 11.7 | 11.7 | 0.1 (−0.1, 0.4)
Mircera subcutaneously every 4 weeks (n=191) | 11.6 | 11.5 | −0.0 (−0.3, 0.2)
Epoetin beta subcutaneously (n=191) | 11.6 | 11.5 | n/a
Study 5
Mircera intravenously every 2 weeks (n=157) | 12.0 | 12.1 | 0.2 (−0.0, 0.4)
Darbepoetin alfa intravenously (n=156) | 11.9 | 11.8 | n/a
Study 6
Mircera intravenously/ subcutaneously every 2 weeks (n=168) | 11.8 | 11.9 | 0.1 (−0.1, 0.4)
Epoetin alfa intravenously/ subcutaneously (n=168) | 11.9 | 11.9 | n/a
*Mircera vs. comparator mean hemoglobin difference in the evaluation period 97.5% CI are shown for
studies that compared two Mircera groups to another ESA (Studies 3 and 4) and 95% CI are shown for the
other studies.
n/a = not applicable
Data are from the per-protocol (primary analysis) population, numbers indicate total patients randomized.

14.2 Pediatric Patients Currently Treated with an ESA

An open-label, multiple dose, multicenter, dose-finding study (NCT00717366) was conducted to determine the dose of intravenous Mircera when converting from treatment with another ESA (epoetin alfa/beta or darbepoetin alfa). The study was conducted in 64 pediatric patients with CKD who were on hemodialysis and who had stable hemoglobin (Hb) levels while previously receiving another ESA. The mean age of the patients was 13 years (age range: 5 to 17 years); 39% were 5 to 11 years of age, and 61% were 12 to 17 years of age. The patient population was 53% male, 72% White, 3% Black, 11% Asian and 14% Other. Eligible patients were administered Mircera intravenously once every 4 weeks for 20 weeks. After the first administration of Mircera, dosage adjustments were permitted to maintain target Hb levels.

Efficacy was established based on the change in Hb concentration (g/dL) between the baseline and evaluation periods. Of the two conversion factors studied, the recommended conversion factor for Mircera [see Dosage and Administration (2.2)] was confirmed based on patients maintaining Hb within target levels. Among the 48 patients who received Mircera dosed using the recommended conversion factor, 9 patients withdrew due to renal transplant, 2 patients withdrew due to administrative reasons, 1 died, and 1 patient refused treatment. One of the 13 patients who withdrew from the study entered the evaluation period (weeks 17 to 21). For the 36 patients who entered the evaluation period and received the dose of Mircera calculated using the recommended conversion factor, the mean change in Hb concentration from baseline between the baseline and the evaluation period was -0.15 g/dL with 95% CI (-0.49, 0.2).

Supportive efficacy results in the group treated with Mircera using the recommended conversion factor demonstrated that 75% of patients maintained Hb values within ± 1 g/dL of baseline and 81% maintained Hb values within 10 to 12 g/dL during the evaluation period. Seventy-seven percent (77%) of patients had a dose adjustment (either a dose decrease, increase or both).

A second open-label, single-arm, multicenter study (NCT03552393) was performed to ascertain the optimal starting dose of Mircera administered subcutaneously for the maintenance treatment of anemia in 40 pediatric patients with CKD on dialysis, or not on dialysis when switching from stable subcutaneous (SC) treatment with epoetin alfa, epoetin beta or darbepoetin alfa. The mean age of patients was 10 years (age range: 4.8months to 17 years); 30 % were less than 5 years of age, 27.5% were 5 to 11 years of age, and 42.5% were 12 years of age or older. The patient population was 58% male, 75% White, 8% Black, and 10% Hispanic or Latino. The starting dose was based on the conversion factors obtained from the intravenous dose-finding study. Mircera was administered SC once every 4 weeks for 20 weeks. Similarly, in this study, efficacy was established based on the change in Hb concentration (g/dL) between the baseline and evaluation periods. The study confirmed that the conversion factors are appropriate. Among the 40 patients who received Mircera, 2 patients (5%) discontinued during the evaluation period. The reasons for discontinuation from the evaluation period were kidney transplant and use of prohibited medication. An additional 4 patients discontinued from the extension period due to kidney transplant. For the 38 patients who had Hb concentration data available during the evaluation period (Weeks 17-21), the mean change in Hb concentration between the baseline and the evaluation period was 0.48 g/dL with 95% CI (0.15, 0.82).

Supportive efficacy results demonstrated that 50% of patients maintained Hb values within ± 1 g/dL of baseline and 63% maintained Hb values within 10 to 12 g/dL during the evaluation period. Dose adjustments (either a dose decrease, increase or both) were reported in 85% of patients.

16 HOW SUPPLIED/STORAGE AND HANDLING

16.1 How Supplied

Mircera (methoxy polyethylene glycol-epoetin beta) injection is available in single-dose prefilled syringes. The syringe plungers are designated with unique colors for each dosage strength. The prefilled syringes are supplied with a 27 gauge, ½ inch needle. To reduce the risk of accidental needlesticks after application, each prefilled syringe is equipped with a needle guard that covers the needle during disposal.

Mircera is available in the following pack sizes:

Single-Dose Prefilled Syringe with a Needle Guard
A 27 Gauge, ½ inch Needle is also provided:

One Prefilled Syringe/Pack | NDC number
30 mcg/0.3 mL | NDC 59353-400-09
50 mcg/0.3 mL | NDC 59353-401-09
75 mcg/0.3 mL | NDC 59353-402-09
100 mcg/0.3 mL | NDC 59353-403-09
120 mcg/0.3 mL | NDC 59353-407-09
150 mcg/0.3 mL | NDC 59353-404-09
200 mcg/0.3 mL | NDC 59353-405-09
250 mcg/0.3 mL | NDC 59353-406-09
360 mcg/0.6 mL | NDC 59353-408-09

16.2 Storage

Store Mircera refrigerated at 2°C to 8°C (36°F to 46°F) in the original carton to protect from light. Do not freeze or shake.

The end-user may store the product at room temperature up to 25°C (77°F) in the original carton up to 30 days. Discard after 30 days.

17 PATIENT COUNSELING INFORMATION

Advise the patient to read the FDA-approved patient labeling (Medication Guide and Instructions for Use).

Inform patients:

- Of the increased risks of mortality, serious cardiovascular reactions, thromboembolic reactions, stroke, and tumor progression [see Warnings and Precautions (5.1, 5.2)].
- To undergo regular blood pressure monitoring, adhere to prescribed anti-hypertensive regimen and follow recommended dietary restrictions.
- To seek medical care immediately if they experience any symptoms of an allergic reaction with use of Mircera [see Warnings and Precautions (5.7)].
- To contact their healthcare provider for new-onset neurologic symptoms or change in seizure frequency.
- Of the need to have regular laboratory tests for hemoglobin.

Administer Mircera under the direct supervision of a healthcare provider or, in situations where a patient or caregiver has been trained to administer Mircera at home, provide instruction on the proper use of Mircera, including instructions to:

- Carefully review the Medication Guide and the Instructions for Use.
- Avoid the reuse of needles, syringes, or unused portions of the Mircera single-dose prefilled syringes and to properly dispose of these items.
  Always keep a puncture-proof disposal container available for the disposal of used syringes and needles.

Manufactured by:
Vifor (International) Inc.
Rechenstrasse 37
9014 St. Gallen
Switzerland

U.S. License No. 2039

MEDICATION GUIDE
MIRCERA® (mir-SER-ah)
(methoxy polyethylene glycol-epoetin beta)
injection, for intravenous or subcutaneous use

Read this Medication Guide:

- before you start Mircera.
- if you are told by your healthcare provider that there is new information about Mircera.
- if you are told by your healthcare provider that you may inject Mircera at home, read this Medication Guide each time you receive a new supply of medicine.

This Medication Guide does not take the place of talking to your healthcare provider about your medical condition or your treatment. Talk with your healthcare provider regularly about the use of Mircera and ask if there is new information about Mircera.

What is the most important information I should know about Mircera?

Mircera may cause serious side effects that can lead to death, including:

For people with cancer:

Mircera is not for use to treat anemia that is caused by cancer chemotherapy. If you have certain cancers, your tumor may grow faster, and you may die sooner if you take Mircera.

For people with anemia from chronic kidney disease (CKD) who take Mircera:

- Serious heart problems, such as heart attack or heart failure, and stroke. You may die sooner if you are treated with Mircera to increase red blood cells (RBCs) to near the same level found in healthy people.
- Blood clots. Blood clots may happen at any time while taking Mircera. Your chance of getting a blood clot that is serious and life threatening is higher if you have cancer. If you are receiving Mircera and you are going to have surgery, talk to your healthcare provider about whether or not you need to take a blood thinner to lessen the chance of blood clots during or following surgery. Blood clots can form in blood vessels (veins), especially in your leg (deep venous thrombosis or DVT). Pieces of a blood clot may travel to the lungs and block the blood circulation in the lungs (pulmonary embolus).
  Call your healthcare provider or get medical help right away if you have any of these symptoms:
  - Chest pain
  - Trouble breathing or shortness of breath
  - Pain in your legs, with or without swelling
  - A cool or pale arm or leg
  - Sudden confusion, trouble speaking, or trouble understanding others’ speech
  - Sudden numbness or weakness in your face, arm or leg, especially on one side of your body
  - Sudden trouble seeing
  - Sudden trouble walking, dizziness, loss of balance or coordination
  - Loss of consciousness (fainting)
  - Hemodialysis vascular access stops working

If you and your healthcare provider decide that you should take Mircera, you should be prescribed the smallest dose of Mircera that is necessary to reduce your chance of needing RBC transfusions.

See “What are the possible side effects of Mircera?” below for more information.

What is Mircera?

Mircera is a prescription medicine used to treat anemia in certain people with chronic kidney disease (CKD). People with anemia have a lower-than-normal number of RBCs. Mircera works like the human protein called erythropoietin to help your body make more RBCs. Mircera is used to reduce or avoid the need for RBC transfusions.

Mircera may be used to treat anemia if it is caused by CKD in:

- adults who may or may not be on dialysis
- children 3 months to 17 years of age who may or may not be on dialysis who are switching from another erythropoiesis-stimulating agent (ESA) after their hemoglobin level is stable

If your hemoglobin level stays too high or if your hemoglobin goes up too quickly, this may lead to serious health problems which may result in death. These serious health problems may happen if you take Mircera, even if you do not have an increase in your hemoglobin level.

Mircera is not used for the treatment of anemia:

- that is caused by cancer chemotherapy
- in place of emergency treatment for anemia (RBC transfusions).

Mircera has not been proven to improve quality of life, fatigue, or well-being.

It is not known if Mircera is safe and effective in children who:

- are under 3 months of age or
- have received another ESA medicine and do not have stable hemoglobin or
- have not been treated with another ESA medicine to correct anemia

Who should not take Mircera?

Do not take Mircera if you:

- Have high blood pressure that is not controlled (uncontrolled hypertension)
- Have been told by your healthcare provider that you have or have ever had a type of anemia called Pure Red Cell Aplasia (PRCA) that starts after treatment with Mircera or other erythropoietin protein medicines
- Have had serious allergic reactions to Mircera. See “What are the possible side effects of Mircera?” for more information.

Before taking Mircera, tell your healthcare provider about all of your medical conditions, including if you:

- Have heart disease.
- Have or develop cancer.
- Have high blood pressure.
- Have had a seizure (convulsion) or stroke.
- Receive dialysis treatment.
- Are pregnant or plan to become pregnant. It is not known if Mircera may harm your unborn baby.
- Are breastfeeding or plan to breastfeed. It is not known if Mircera passes into your breast milk.

Tell your healthcare provider about all of the medicines you take, including prescription and over-the-counter medicines, vitamins, and herbal supplements.

How should I take Mircera?

- If you or your caregiver has been trained to give Mircera shots (injections) at home:
  - Be sure that you read, understand, and follow the “Instructions for Use” that come with Mircera.
  - Take Mircera exactly as your healthcare provider tells you to. Do not change the dose of Mircera unless told to by your healthcare provider.
  - Your healthcare provider may lower your dose, or temporarily stop Mircera and restart it at a lower dose, if your hemoglobin levels get too high during treatment.
  - Your healthcare provider will show you how much Mircera to use, how to inject it, how often it should be injected, and how to safely throw away the used prefilled syringes and needles.
  - If you take more than your prescribed dose of Mircera, call your healthcare provider right away for instructions on what to do.
- During treatment with Mircera, continue to follow your healthcare provider’s instructions for diet, dialysis, and medicines, including medicines for high blood pressure.
- Have your blood pressure checked as instructed by your healthcare provider.
- Your healthcare provider will do regular blood tests during treatment to check your hemoglobin levels.

What are the possible side effects of Mircera?

Mircera may cause serious side effects, including:

- See “What is the most important information I should know about Mircera?”
- High blood pressure. High blood pressure is a common side effect of Mircera in patients with chronic kidney disease. Your blood pressure may go up or be difficult to control with blood pressure medicine while taking Mircera. This can happen even if you have never had high blood pressure before. Your healthcare provider should check your blood pressure often. If your blood pressure does go up, your healthcare provider may prescribe new or more blood pressure medicine.
- Seizures. If you have any seizures while taking Mircera, get medical help right away and tell your healthcare provider.
- No response or loss of your hemoglobin response to Mircera. If your hemoglobin does not increase, or if the increase cannot be maintained, your healthcare provider will look for the cause of the problem. Your dose of Mircera or other medicines may need to be changed.
- Antibodies to Mircera. Your body may make antibodies to Mircera. These antibodies can block or lessen your body’s ability to make RBCs and cause you to have severe anemia. Call your healthcare provider if you have unusual tiredness, lack of energy, dizziness or fainting. You may need to stop taking Mircera.
- Serious allergic reaction. Serious allergic reactions can cause itching, shortness of breath, wheezing, dizziness and fainting because of a drop in blood pressure, swelling around your mouth or eyes, fast pulse, or sweating. If you have a serious allergic reaction, stop using Mircera and call your healthcare provider or get emergency medical help right away.
- Severe skin reactions. Severe skin reactions can happen during treatment. Signs and symptoms of severe skin reactions with Mircera may include skin rash with itching, hives, blisters, skin sores, peeling, or areas of skin coming off. If you develop any signs or symptoms of skin reactions, stop using Mircera and call your healthcare provider or get medical help right away.

Common side effects of Mircera include:

- diarrhea
- pain or swelling (inflammation) in your nose or throat (nasopharyngitis).

These are not all of the possible side effects of Mircera. Your healthcare provider can give you a more complete list. Tell your healthcare provider about any side effects that bother you or that do not go away.

Call your doctor for medical advice about side effects. You may report side effects to FDA at 1-800-FDA-1088.

How should I store Mircera?

- Store Mircera prefilled syringes in the refrigerator between 36°F to 46°F (2°C to 8°C).
- Do not freeze or shake Mircera.
- Keep Mircera in the original carton to protect it from light.
- Mircera prefilled syringes may be stored at room temperature up to 77°F (25°C) for no more than 30 days.
- Throw away (discard) Mircera after 30 days if it has been stored at room temperature.

Keep Mircera and all medicines out of the reach of children.

General information about the safe and effective use of Mircera.

Medicines are sometimes prescribed for purposes other than those listed in a Medication Guide. Do not use Mircera for a condition for which it was not prescribed. Do not give Mircera to other people, even if they have the same symptoms that you have. It may harm them. You can ask your pharmacist or healthcare provider for information about Mircera that is written for health professionals.

What are the ingredients in Mircera?

Active ingredients: methoxy polyethylene glycol-epoetin beta

Inactive ingredients: mannitol, methionine, poloxamer 188, sodium phosphate monobasic monohydrate, and sodium sulfate.
Manufactured by:
Vifor (International) Inc.
Rechenstrasse 37
9014 St. Gallen
Switzerland

U.S. License No. 2039
U.S. Toll-free: 1-800–576-8295
Info_MirceraUS@viforpharma.com
Copyright © 2018 Vifor (International) Inc. All rights reserved.

This Medication Guide has been approved by the U.S. Food and Drug Administration.

Revised: 06/2024

INSTRUCTIONS FOR USE
MIRCERA® (mir-SER-ah)
(methoxy polyethylene glycol-epoetin beta)
injection, for intravenous or subcutaneous use
single-dose prefilled syringe

Read the Medication Guide that comes with Mircera for the most important information you need to know.

This Instructions for Use explains how to give yourself or another individual an injection of Mircera using the single-dose prefilled syringe. Be sure that you read, understand and follow these instructions before injecting a dose of Mircera and each time you get your prescription refilled, so that you are able to use the prefilled syringe correctly and safely.

Your healthcare provider should show you how to correctly prepare and inject Mircera using the single-dose prefilled syringe before you use it for the first time. Ask your healthcare provider or pharmacist if you have any questions about Mircera.

When you receive your Mircera prefilled syringes, make sure that:

- The name Mircera appears on the pack.
- The pack is not damaged. Do not use Mircera if the prefilled syringe, the pack or the plastic tray containing the prefilled syringe appears to be damaged.
- The expiration date on the pack has not passed. Do not use Mircera after the expiration date on the pack.
- The strength (mcg/mL) on the Mircera pack is the same as the strength (mcg/mL) prescribed by your healthcare provider. Mircera prefilled syringes come in several different strengths measured in mcg/mL. Depending on your prescribed dose you may:
  - receive more than one strength of Mircera prefilled syringes
  - need to give more than one injection to receive a complete dose

Important Information You Need to Know Before Injecting Mircera:

- Only use Mircera prefilled syringes if you have been prescribed this medicine by your healthcare provider.
- Your healthcare provider may decide that you or a caregiver may give Mircera at home by an injection under your skin (subcutaneous) or by an intravenous injection. Your healthcare provider or nurse will train you how to prepare and inject Mircera properly. It is important that you do not try to give Mircera unless you or your caregiver has received training from your healthcare provider.
- Children under 17 years of age should not inject themselves with Mircera. An adult caregiver should prepare and give Mircera injections to the child.
- Keep the Mircera prefilled syringe in the sealed pack until you are ready to use it.
- Do not use the syringe if the medicine is cloudy, hazy, or contains particles.
- Do not attempt to take the syringe apart.
- Do not hold or pull the prefilled syringe by the plunger.
- Do not remove the needle shield until you are ready to give an injection.
- Do not inject through clothing.
- Do not swallow the medicine in the syringe.
- Do not touch the activation guards before use (see Figure A). Touching them may cause the needle safety device to be released too early and make the prefilled syringe unusable.
- Do not try to inject a dose that is smaller than the dose (a partial dose) contained in the prefilled syringe.

Throw away (dispose of) the used Mircera prefilled syringe right away after use. Do not reuse a Mircera prefilled syringe or needle. See “Disposing of used Mircera prefilled syringes and needles” at the end of this Instructions for Use.

Storing Mircera

How should I store Mircera?

- Store Mircera in the refrigerator between 36°F to 46°F (2°C to 8°C).
- If a refrigerator is not available, Mircera prefilled syringes can be stored at room temperature between 68°F to 77°F (20°C to 25°C) for no more than 30 days.
- Throw away Mircera after 30 days if it has been stored at room temperature.
- Do not freeze Mircera. Do not use Mircera that has been frozen.
- Keep Mircera in the original package to protect it from light.
- Do not shake Mircera.

Keep Mircera and all medicines out of the reach of children.

Materials (supplies)

Materials included in the Mircera prefilled syringe pack (Figure A):

- A prefilled syringe containing Mircera
- A separate injection needle

Figure A

Materials not included in the Mircera prefilled syringe pack (Figure B):

Figure B

Important: Follow these instructions exactly to help avoid infections.

Preparing for a Mircera injection:

1. Gather all of the materials you will need for an injection on a clean, well-lit, flat work surface such as a table.
2. Allow the syringe to reach room temperature:
  Carefully remove your prescribed pack of Mircera from the refrigerator (see Figure C).
  1. Keep the prefilled syringe in the pack to protect it from light and allow it to reach room temperature for about 30 minutes. If the prefilled syringe does not reach room temperature, this could cause your injection to feel uncomfortable, and it may be difficult to push (depress) the plunger.
  2. Do not warm up the prefilled syringe in any other way.

Figure C

3. Open the pack and remove the plastic tray containing the Mircera prefilled syringe without peeling back the protective film (see Figure D).

Figure D

4. Wash your hands well with soap and warm water (see Figure E).

Figure E

5. Remove and inspect the prefilled syringe.
  Open the plastic tray by peeling back the protective film. Remove the prefilled syringe by holding the syringe by the device body (see Figure F). Do not touch the activation guards.
  1. Only handle the prefilled syringe by the device body. Touching the activation guards could cause the needle safety device to be released too early.
  2. Remove the needle from the plastic tray.

Figure F

6. Inspect the medicine and prefilled syringe (see Figure G).
  Do not use the prefilled syringe if:
  1. The prefilled syringe has been dropped or shaken.
  2. Any part of the prefilled syringe appears cracked or damaged.
  3. The liquid is foamy, cloudy, hazy or contains particles.
  4. The expiration date has passed.

Figure G

Attach needle to prefilled syringe:

7. Grasp the prefilled syringe in the middle of the syringe body with one hand. With the other hand, hold the rubber tip cap firmly, and remove the rubber tip cap from the prefilled syringe (bend and pull) (see Figure H).
  1. Throw away (dispose of) the rubber tip cap in the sharps disposal container
  2. Do not touch the activation guard.
  3. Do not push or pull on the plunger.
Place the prefilled syringe on your work surface. Be careful that the tip of the prefilled syringe does not touch anything. If the tip of the prefilled syringe touches anything, dispose of the prefilled syringe (see “Disposing of used Mircera prefilled syringes and needles” below) and use a new prefilled syringe and needle for the injection.

Figure H

8. Grasp the packaged needle firmly in both hands.
  Break the seal of the needle, using a twisting motion, and remove the plastic needle cap (see Figure I).
  1. Throw away (dispose of) the needle cap right away in the sharps disposal container.
  2. Do not remove the needle shield that protects the needle.

Figure I

9. Attach the needle to the prefilled syringe by pushing it firmly straight onto the prefilled syringe and by twisting or turning it slightly (see Figure J).

Figure J

10. Put the prefilled syringe on its side with the needle shield on. This will keep the needle from touching anything before you use it.

Giving the Mircera injection
Follow your healthcare provider’s instructions for how you should inject Mircera.

Giving Mircera as a subcutaneous (under the skin) injection:

If your healthcare provider tells you to inject Mircera as a subcutaneous (under your skin) injection, give your dose as described below.

Selecting and preparing a subcutaneous injection site:
After you prepare the prefilled syringe as described in steps 7 to 10 above:

11. Choose an injection site as shown in Figure K.
  The three sites where you can inject Mircera include:
  1. the outer area of the upper arms (only if someone else is giving you the injection)
  2. the front of the middle thighs
  3. the abdomen, except for the 2-inch area around the navel (belly button)
Choose a new injection site each time you inject Mircera, at least 1-inch from the area you used for the previous injection. This helps to avoid soreness at any one site.
Do not inject Mircera into moles or into an area of your body that is tender, red, bruised, or hard, that has scars or stretch marks, or is not intact.
Do not inject into areas that could be irritated by a belt or waistband.

Figure K

12. Clean the injection site with an alcohol swab (see Figure L). Throw away the alcohol swab immediately after use.
  1. Let the skin dry for about 10 seconds.
  2. Do not touch this area again before giving the injection.
  3. Do not fan or blow on the clean area.

Figure L

13. Hold the prefilled syringe firmly with one hand in the middle of the syringe body and pull off the needle shield with the other hand (see Figure M). Throw away the needle shield in the sharps disposal container.
  1. Do not touch the needle or let it touch any surface.
  2. You may see a drop of liquid at the end of the needle. This is normal.
  3. Do not reattach the needle shield after removal.

Figure M

14. Check the prefilled syringe for air bubbles. To remove air bubbles from the prefilled syringe, hold the syringe by the body with the needle pointing up. Tap the prefilled syringe body gently to bring the air bubbles to the top
  (see Figure N).

Figure N

15. Push the plunger up gently and slowly until you see a drop of liquid coming out of the needle (see Figure O).

Figure O

16. Find a comfortable position to give an injection of Mircera.
Hold the prefilled syringe in the hand that you will use to inject Mircera. Use the other hand to pinch a fold of loose skin at the cleaned injection site (see Figure P).

Figure P

17. Hold the prefilled syringe like a pencil. Fully and carefully insert the needle into the skin in a quick “dart-like” motion. Insert straight up and down (90-degree angle) into the skin. Keep the prefilled syringe in the skin and slowly let go of the pinch of skin.
  1. Do not move the needle while it is inserted in the skin.
Slowly push the plunger with your thumb all the way down while holding the prefilled syringe with your first finger and your middle finger against the finger grips until all the medicine is injected. The plunger rod should be fully pushed down (depressed) until you hear a click indicating the activation of the needle guard (see Figure Q).
  - Do not release the plunger before the end of injection or before the plunger is completely pushed down (depressed).
  - The plastic needle guard (a safety guard to prevent accidental needle sticks) will not move forward to cover the needle unless the full dose is given.

Figure Q

18. Take the needle out of the skin without releasing the plunger (see Figure R).

Figure R

19. Release the plunger after removing the needle from the skin. This will allow the prefilled syringe to move back until the entire needle is covered with the needle guard (see Figure S).

Figure S

20. Now the tear-off label can be removed, if necessary to keep a record of the dose taken (see Figure T).

Figure T

21. After the injection: Place a sterile cotton ball or gauze over the injection site and press for several seconds (see Figure U). Throw away the cotton ball or gauze immediately after use.
  1. Do not rub the injection site with an unclean hand or cloth.
If needed, you may cover the injection site with a small adhesive bandage.

Figure U

22. Dispose of the used prefilled syringe: Throw away (dispose of) the used prefilled syringe and the attached needle in the sharps container right away. Do not reuse your prefilled syringe or needle. See “Disposing of used Mircera prefilled syringes and needles” below.

Giving Mircera as an intravenous injection:
If your healthcare provider has told you to and has shown you or your caregiver how to inject Mircera intravenously, give your dose as described below:

- Mircera can be injected in your vein through a special access (venous) port placed by your healthcare provider. This type of Mircera injection is called an intravenous injection.
- If you have a hemodialysis vascular access, make sure that the venous port is working by checking it as your healthcare provider has shown you. Call your healthcare provider right away if you are having any problems or if you have any questions.

After you prepare the prefilled syringe as described in steps 7 to 10 above:

1. Clean the venous port of the hemodialysis tubing with an alcohol swab as instructed by your healthcare provider or the manufacturer (see Figure A). Throw away the alcohol swab immediately after use.

Figure A

2. Hold the prefilled syringe firmly with one hand and pull off the needle shield with the other hand (see Figure B). Throw away the needle shield in the sharps disposal container.
  1. Do not touch the needle or let it touch any surface.
  2. You may see a drop of liquid at the end of the needle. This is normal.
  3. Do not reattach the needle shield after removal.

Figure B

3. Check the prefilled syringe for air bubbles. To remove air bubbles from the prefilled syringe, hold the prefilled syringe by the device body with the needle pointing up. Tap the prefilled syringe body gently to bring the air bubbles to the top (see Figure C).

Figure C

4. Push the plunger up gently and slowly until you see a drop of liquid coming out of the needle (see Figure D).

Figure D

5. Insert the needle on the prefilled syringe into the cleaned venous port (see Figure E). Do not touch the injection site of the venous port.
  1. Do not move the needle while it is inserted in the port.

Figure E

6. Push the plunger with your thumb all the way down, while holding the prefilled syringe with your first finger and your middle finger against the finger grips until all the medicine is injected. The plunger rod should be fully pushed down (depressed) until you hear a click indicating the activation of the needle guard (see Figure F).
  1. Do not release the plunger before the end of injection or before the plunger is completely pushed down (depressed).
  2. The plastic needle guard (a safety guard to prevent accidental needle sticks) will not move forward to cover the needle unless the full dose is given.
7. Pull back on the prefilled syringe and remove the needle from the venous port without releasing the plunger.

Figure F

8. Release the plunger after removing the needle from the port. This will allow the prefilled syringe to move back until the entire needle is covered with the needle guard (see Figure G).

Figure G

9. Now the tear-off label can be removed, if necessary to keep a record of the dose taken (see Figure H).

Figure H

10. Dispose of the used Mircera prefilled syringe:
  Throw away (dispose of) the used prefilled syringe and the attached needle in the sharps container right away. Do not reuse your prefilled syringe and needle. See “Disposing of used prefilled syringes and needles” below.

Disposing of used Mircera prefilled syringes and needles:
2. Put your used needles and prefilled syringes in an FDA-cleared sharps disposal container right away after use. Do not throw away (dispose of) loose needles and prefilled syringes in your household trash.
3. If you do not have an FDA-cleared sharps disposal container, you may use a household container that is:
  - made of heavy-duty plastic,
  - can be closed with a tight-fitting, puncture-resistant lid, without sharps being able to come out,
  - upright and stable during use,
  - leak-resistant, and
  - properly labeled to warn of hazardous waste inside the container.
4. When your sharps disposal container is almost full, you will need to follow your community guidelines for the right way to dispose of your sharps disposal container. There may be state or local laws about how you should throw away used needles, syringes and prefilled injectors. For more information about safe sharps disposal, and for specific information about sharps disposal in the state that you live in, go to the FDA’s website at: http://www.fda.gov/safesharpsdisposal.
5. Do not dispose of your used sharps disposal container in your household trash unless your community guidelines permit this. Do not recycle your used sharps disposal container.

Always keep the sharps disposal container out of the reach of children.

This Instructions for Use has been approved by the U.S. Food and Drug Administration.

Vifor (International) Inc., Rechenstrasse 37, 9014 St. Gallen, Switzerland, U.S. License No. 2039
U.S. Toll-free: 1-800–576-8295, Info_MirceraUS@viforpharma.com,

Copyright 2016 Vifor (International) Inc. All rights reserved.
Revised: April 2024

PRINCIPAL DISPLAY PANEL - 30 mcg / 0.3 mL Carton Label

NDC 59353-400-09

MIRCERA®
(methoxy polyethylene glycol-epoetin beta)

30 mcg / 0.3 mL

Sterile Solution
For intravenous or subcutaneous use only
Single-dose only. Discard unused portion.
Single-dose Prefilled Syringe with 27 Gauge Needle

KEEP REFRIGERATED

PHARMACIST: Each patient is required to receive the enclosed Medication Guide

Rx only

CSL Vifor

PRINCIPAL DISPLAY PANEL - 50 mcg / 0.3 mL Carton Label

NDC 59353-401-09

MIRCERA®
(methoxy polyethylene glycol-epoetin beta)

50 mcg / 0.3 mL

Sterile Solution
For intravenous or subcutaneous use only
Single-dose only. Discard unused portion.
Single-dose Prefilled Syringe with 27 Gauge Needle

KEEP REFRIGERATED

PHARMACIST: Each patient is required to receive the enclosed Medication Guide

Rx only

CSL Vifor

PRINCIPAL DISPLAY PANEL - 75 mcg / 0.3 mL Carton Label

NDC 59353-402-09

MIRCERA®
(methoxy polyethylene glycol-epoetin beta)

75 mcg / 0.3 mL

Sterile Solution
For intravenous or subcutaneous use only
Single-dose only. Discard unused portion.
Single-dose Prefilled Syringe with 27 Gauge Needle

KEEP REFRIGERATED

PHARMACIST: Each patient is required to receive the enclosed Medication Guide

Rx only

CSL Vifor

PRINCIPAL DISPLAY PANEL - 100 mcg / 0.3 mL Carton Label

NDC 59353-403-09

MIRCERA®
(methoxy polyethylene glycol-epoetin beta)

100 mcg / 0.3 mL

Sterile Solution
For intravenous or subcutaneous use only
Single-dose only. Discard unused portion.
Single-dose Prefilled Syringe with 27 Gauge Needle

KEEP REFRIGERATED

PHARMACIST: Each patient is required to receive the enclosed Medication Guide

Rx only

CSL Vifor

PRINCIPAL DISPLAY PANEL - 120 mcg / 0.3 mL Carton Label

NDC 59353-407-09

MIRCERA®
(methoxy polyethylene glycol-epoetin beta)

120 mcg / 0.3 mL

Sterile Solution
For intravenous or subcutaneous use only
Single-dose only. Discard unused portion.
Single-dose Prefilled Syringe with 27 Gauge Needle

KEEP REFRIGERATED

PHARMACIST: Each patient is required to receive the enclosed Medication Guide

Rx only

CSL Vifor

PRINCIPAL DISPLAY PANEL - 150 mcg / 0.3 mL Carton Label

NDC 59353-404-09

MIRCERA®
(methoxy polyethylene glycol-epoetin beta)

150 mcg / 0.3 mL

Sterile Solution
For intravenous or subcutaneous use only
Single-dose only. Discard unused portion.
Single-dose Prefilled Syringe with 27 Gauge Needle

KEEP REFRIGERATED

PHARMACIST: Each patient is required to receive the enclosed Medication Guide

Rx only

CSL Vifor

PRINCIPAL DISPLAY PANEL - 200 mcg / 0.3 mL Carton Label

NDC 59353-405-09

MIRCERA®
(methoxy polyethylene glycol-epoetin beta)

200 mcg / 0.3 mL

Sterile Solution
For intravenous or subcutaneous use only
Single-dose only. Discard unused portion.
Single-dose Prefilled Syringe with 27 Gauge Needle

KEEP REFRIGERATED

PHARMACIST: Each patient is required to receive the enclosed Medication Guide

Rx only

CSL Vifor

PRINCIPAL DISPLAY PANEL - 250 mcg / 0.3 mL Carton Label

NDC 59353-406-09

MIRCERA®
(methoxy polyethylene glycol-epoetin beta)

250 mcg / 0.3 mL

Sterile Solution
For intravenous or subcutaneous use only
Single-dose only. Discard unused portion.
Single-dose Prefilled Syringe with 27 Gauge Needle

KEEP REFRIGERATED

PHARMACIST: Each patient is required to receive the enclosed Medication Guide

Rx only

Vifor Pharma

PRINCIPAL DISPLAY PANEL - 360 mcg / 0.6 mL Carton Label

NDC 59353-408-09

MIRCERA®
(methoxy polyethylene glycol-epoetin beta)

360 mcg / 0.6 mL

Sterile Solution
For intravenous or subcutaneous use only
Single-dose only. Discard unused portion.
Single-dose Prefilled Syringe with 27 Gauge Needle

KEEP REFRIGERATED

PHARMACIST: Each patient is required to receive the enclosed Medication Guide

Rx only

Vifor Pharma